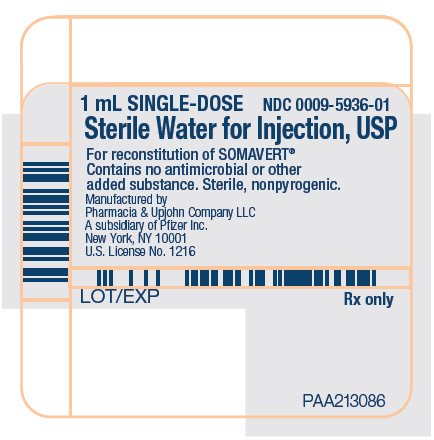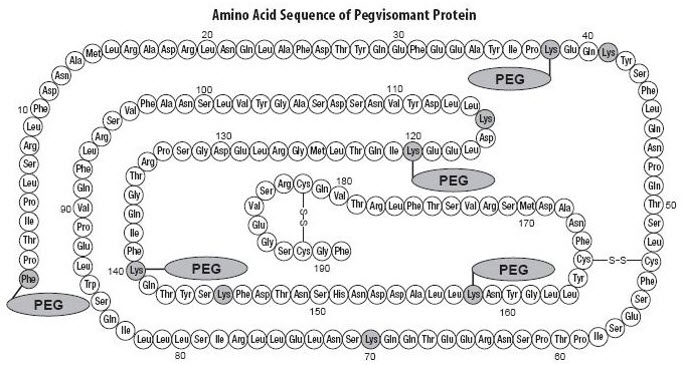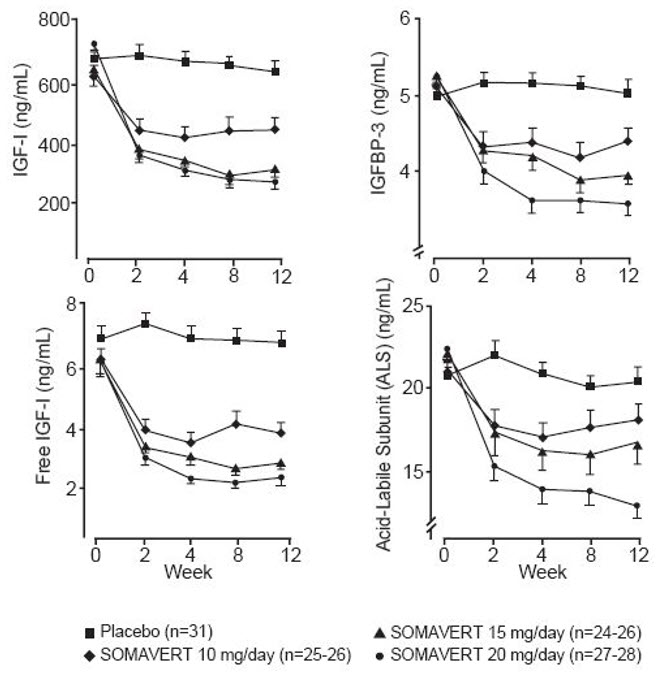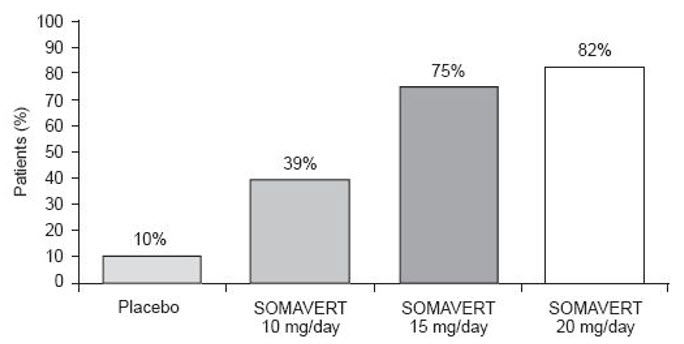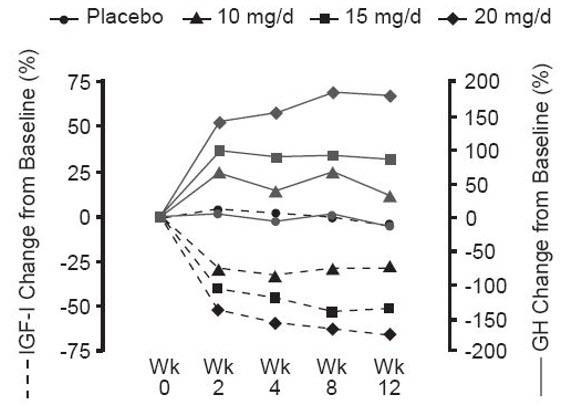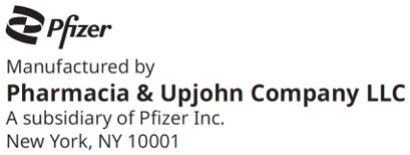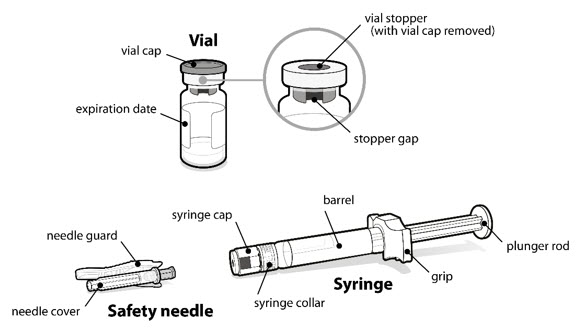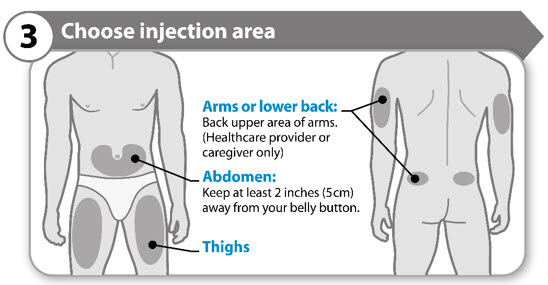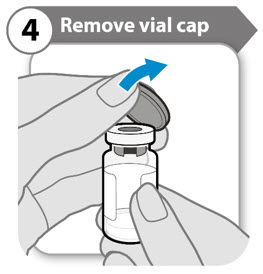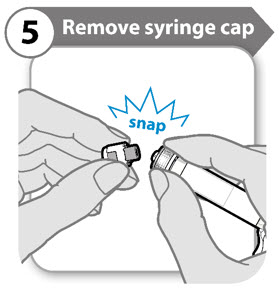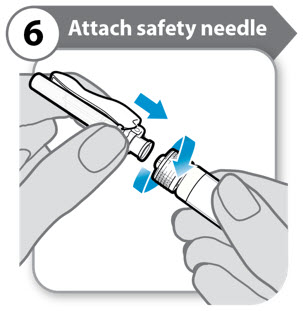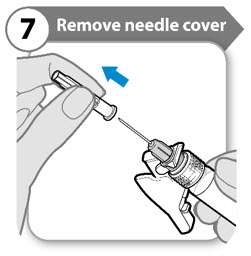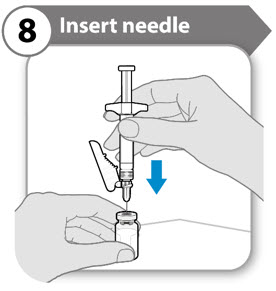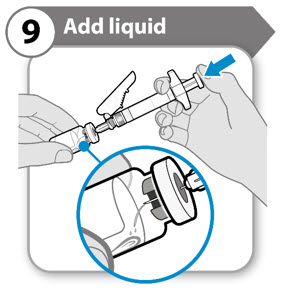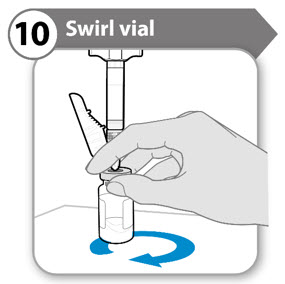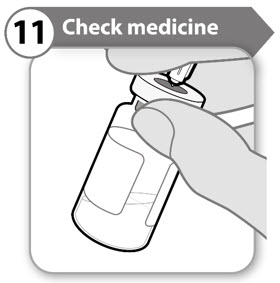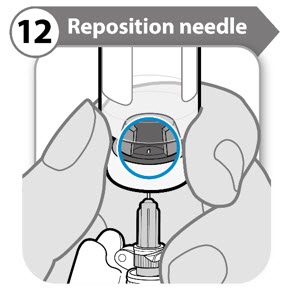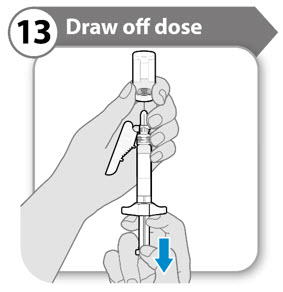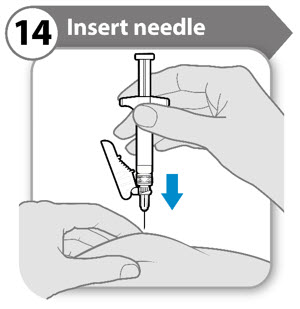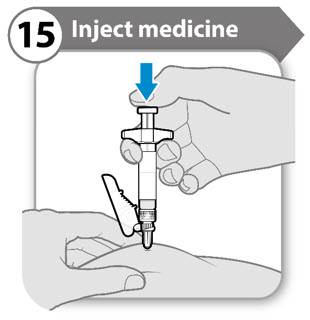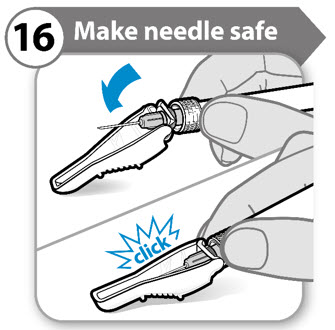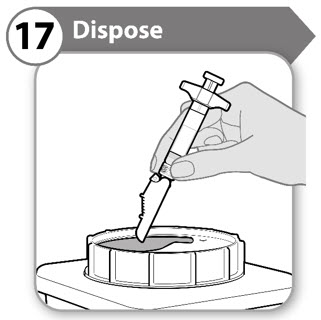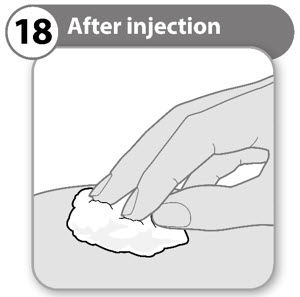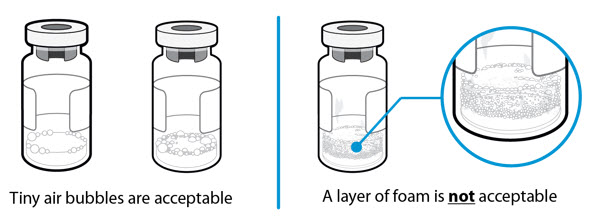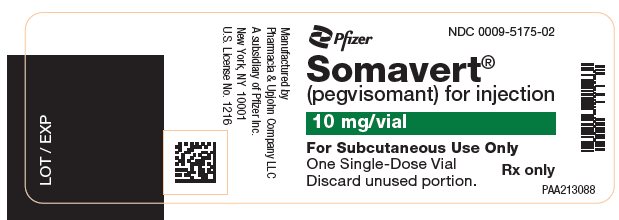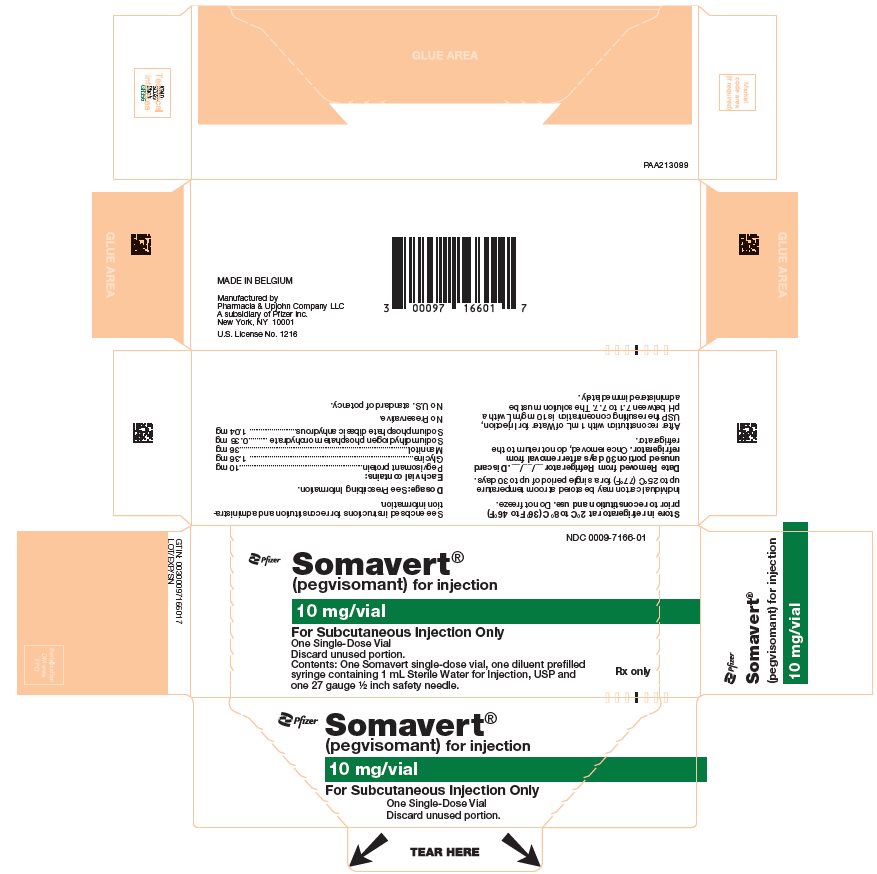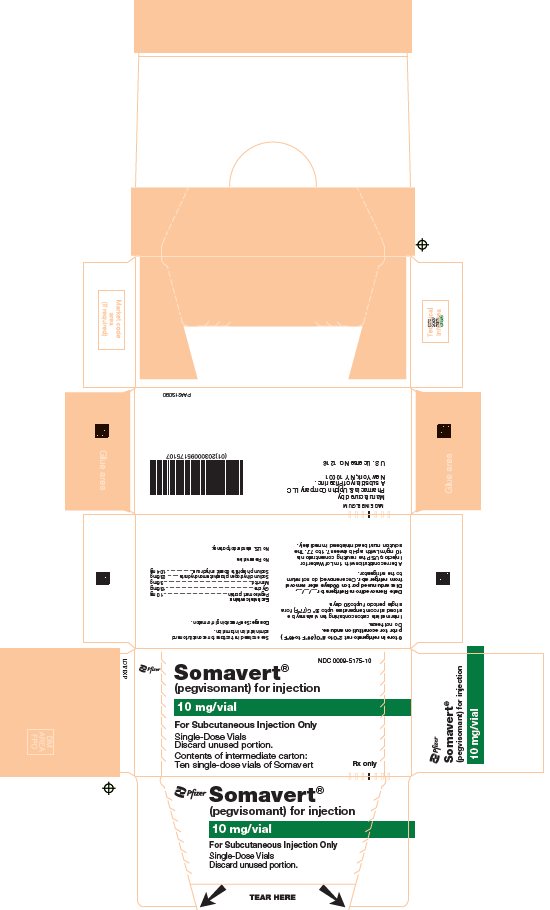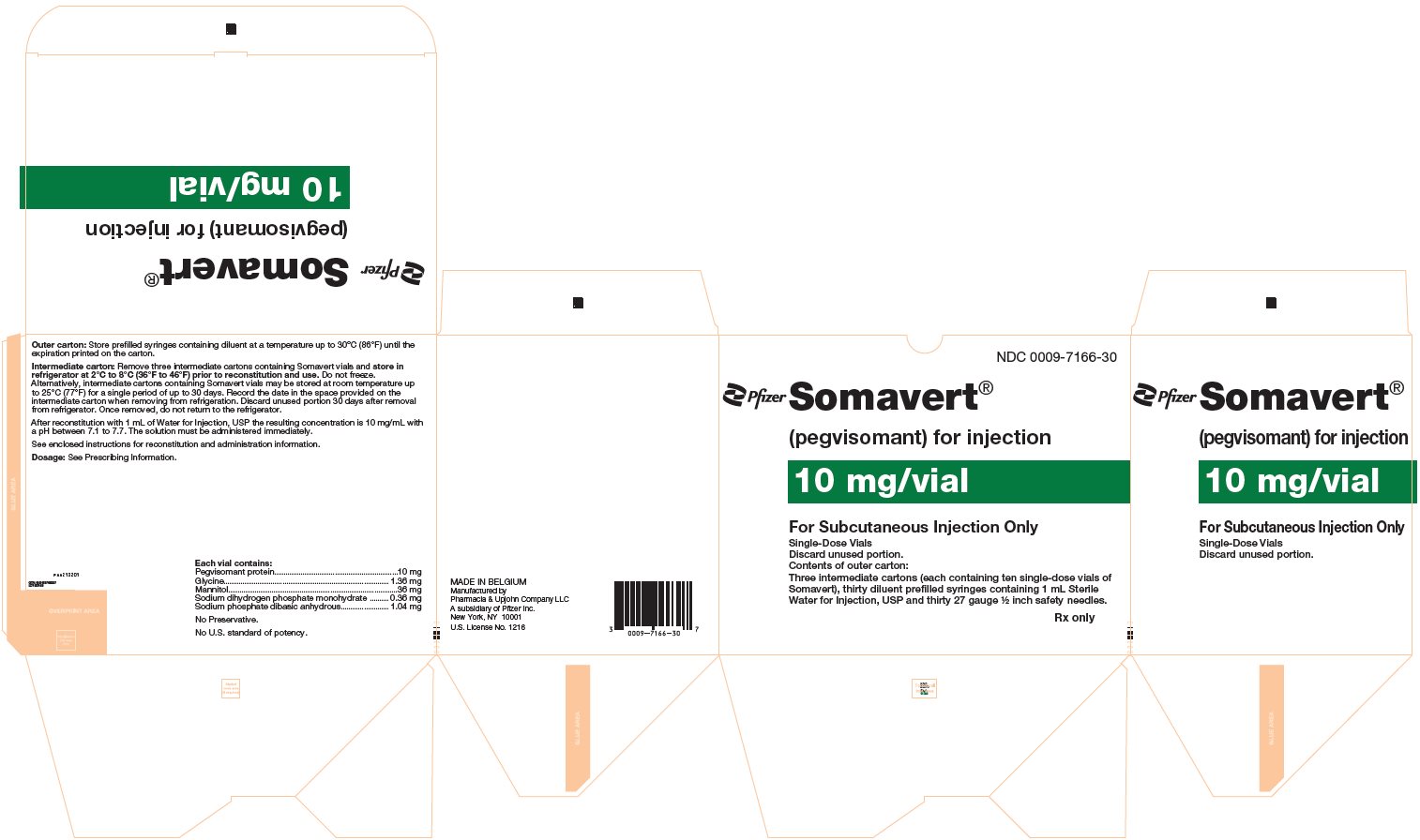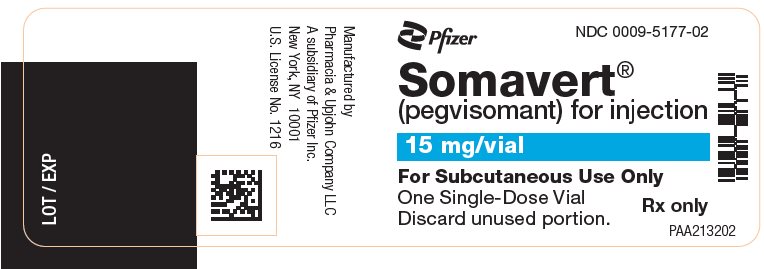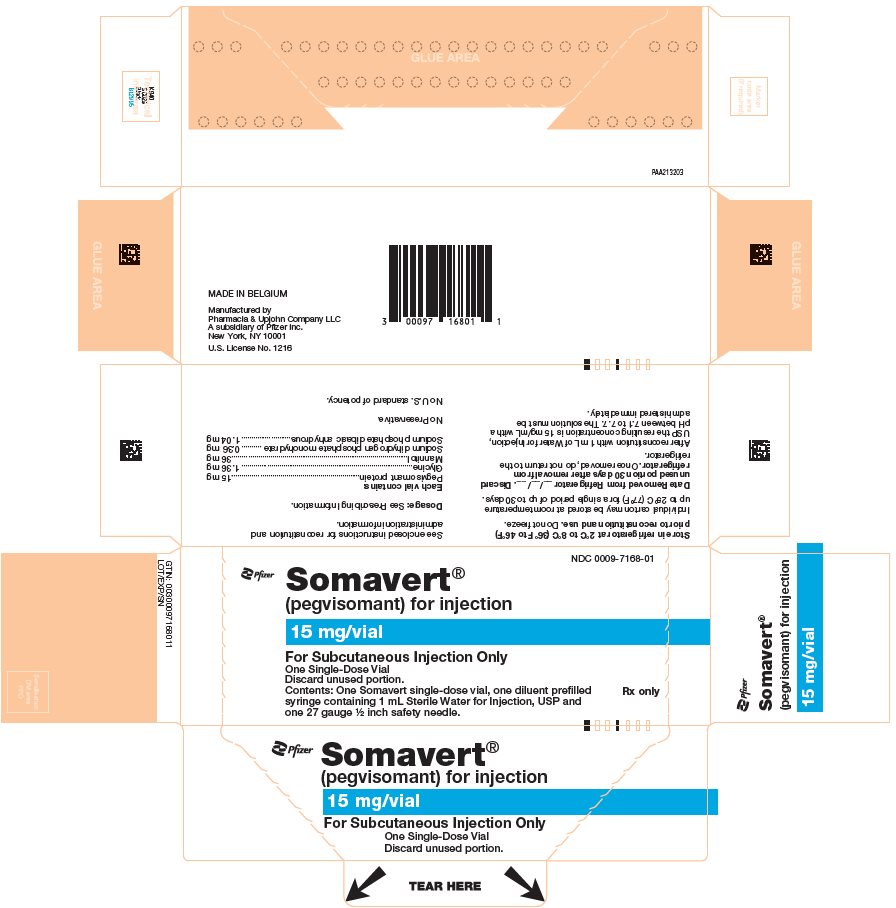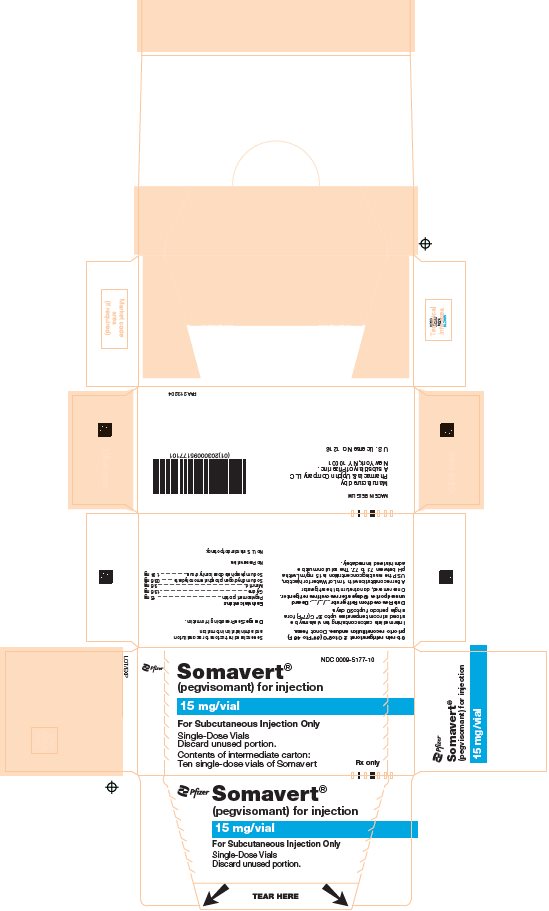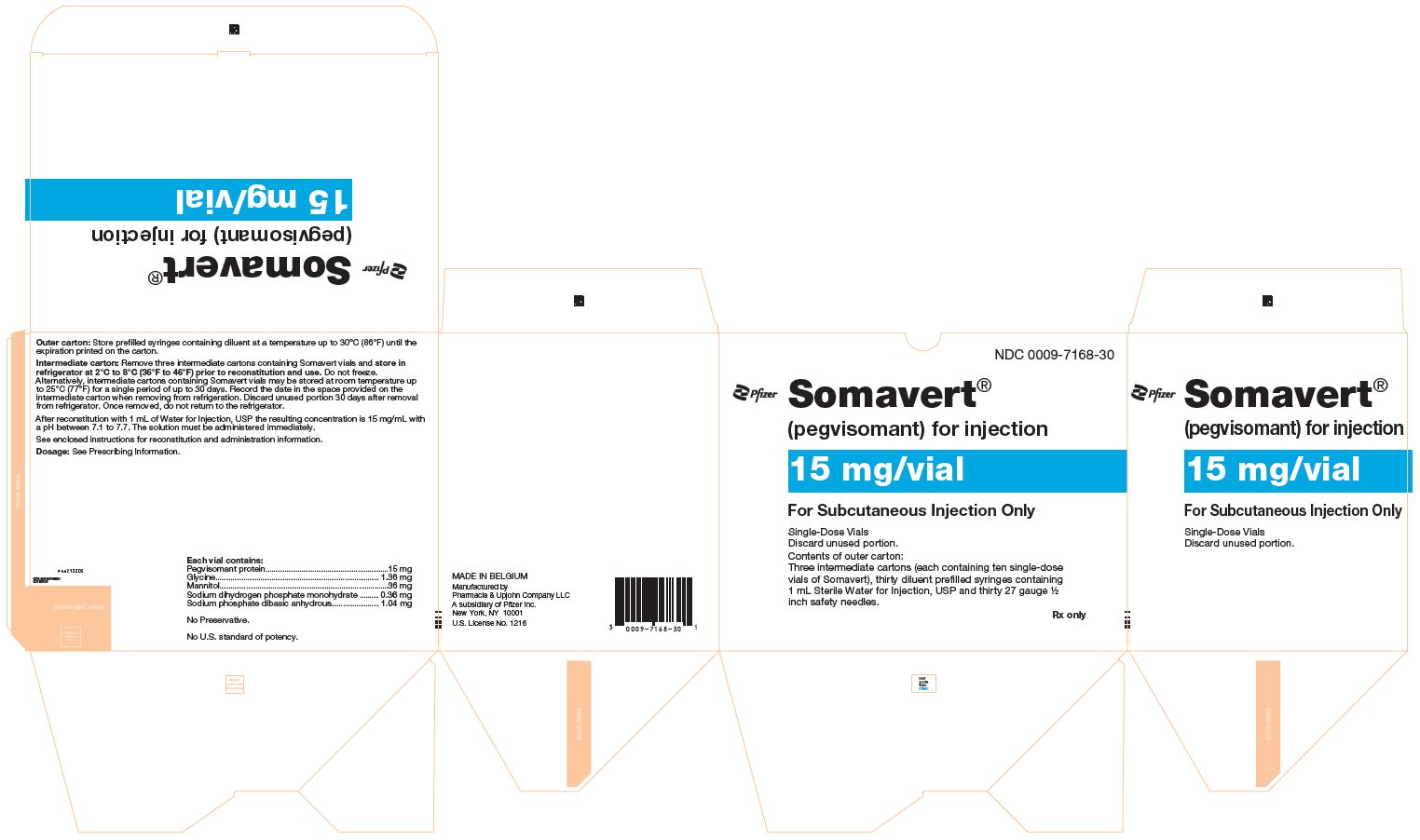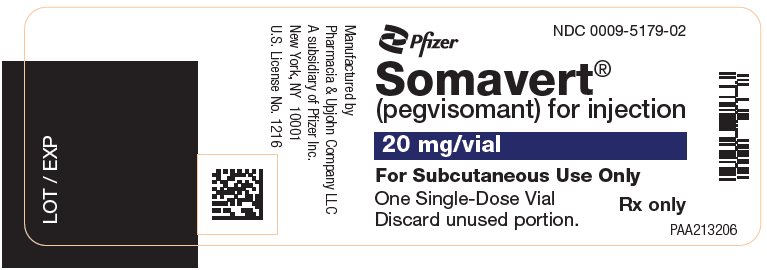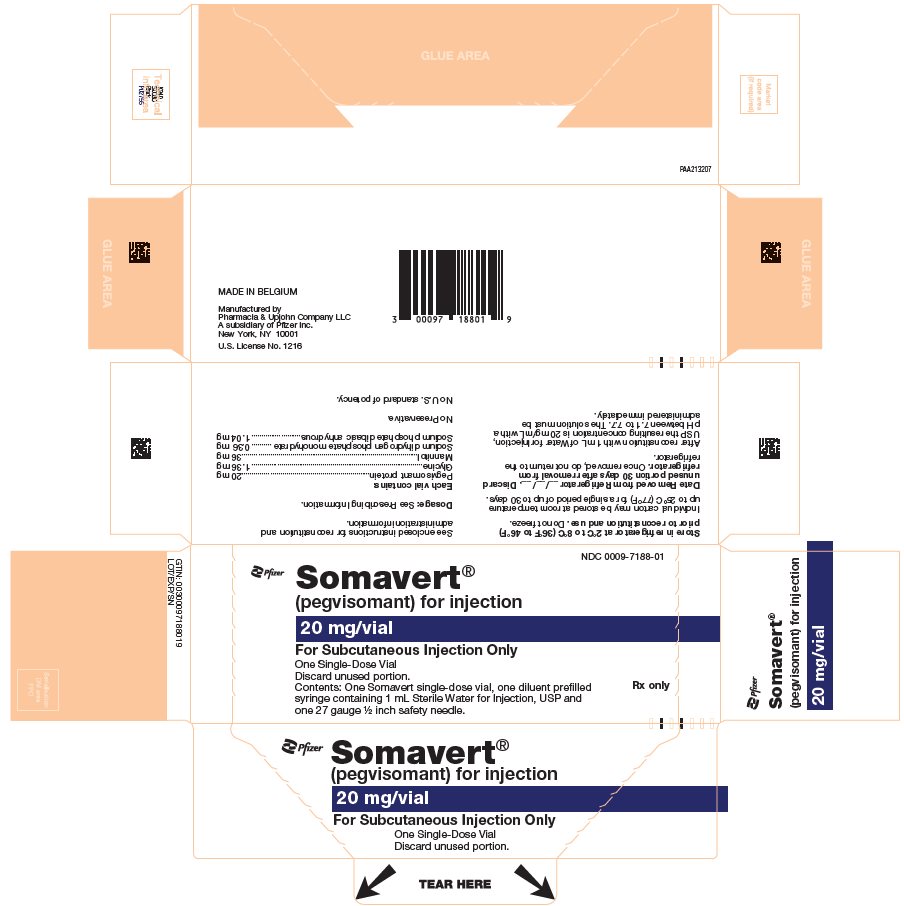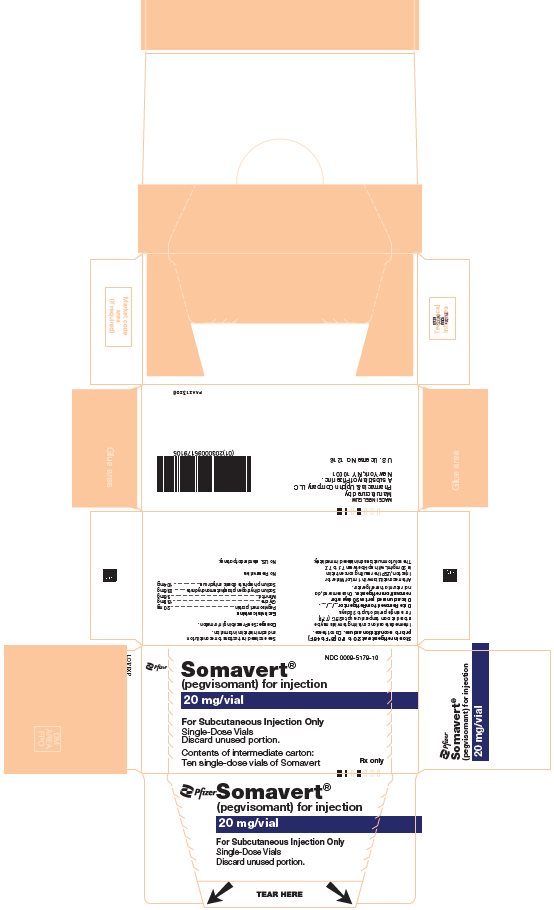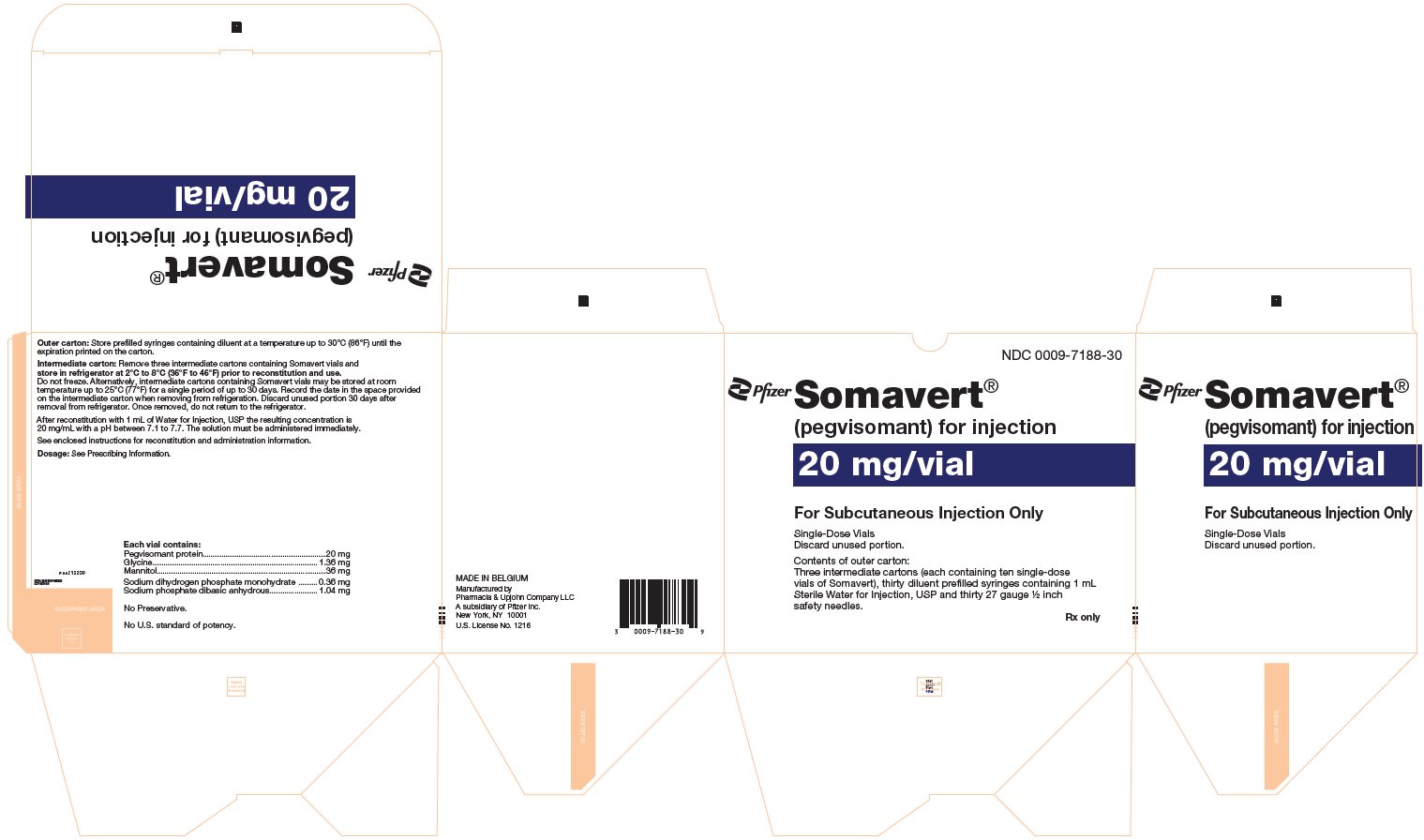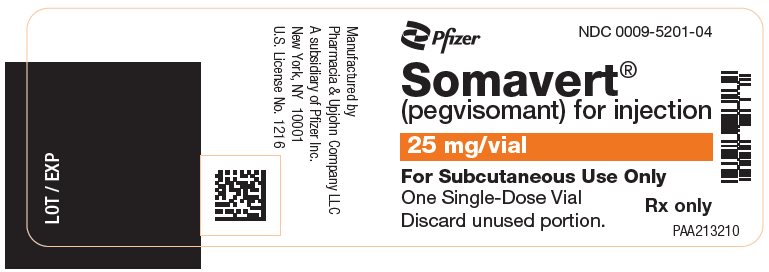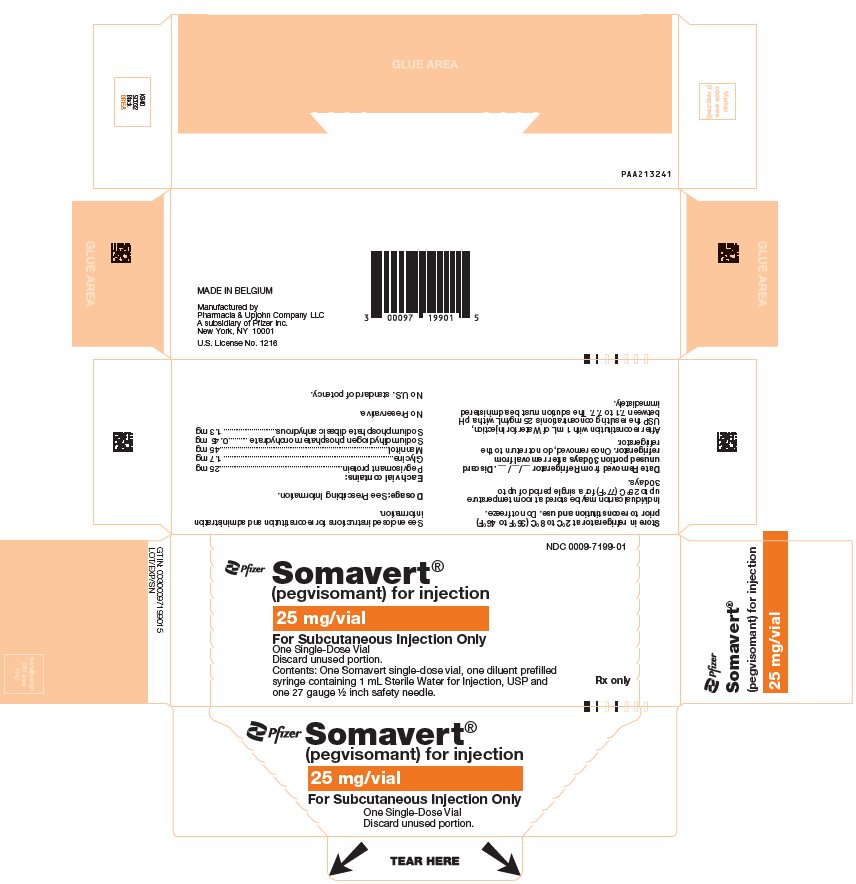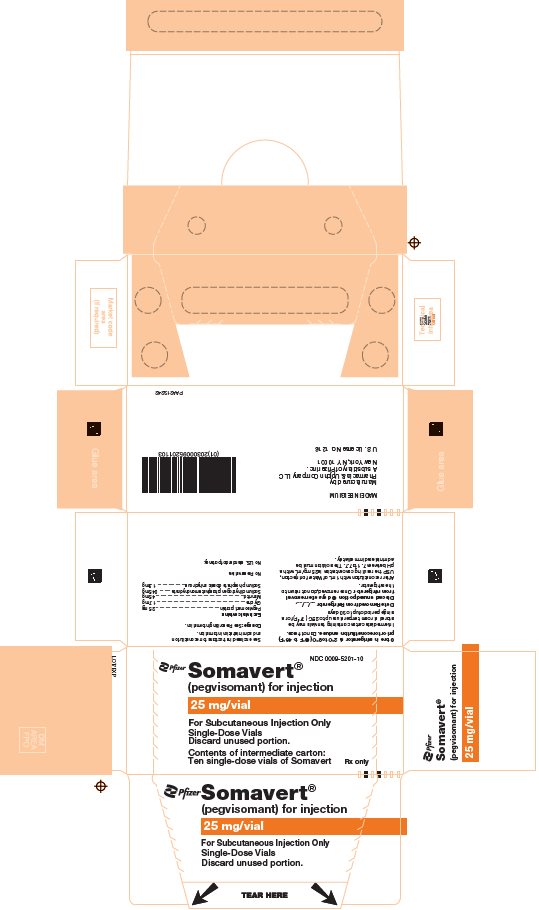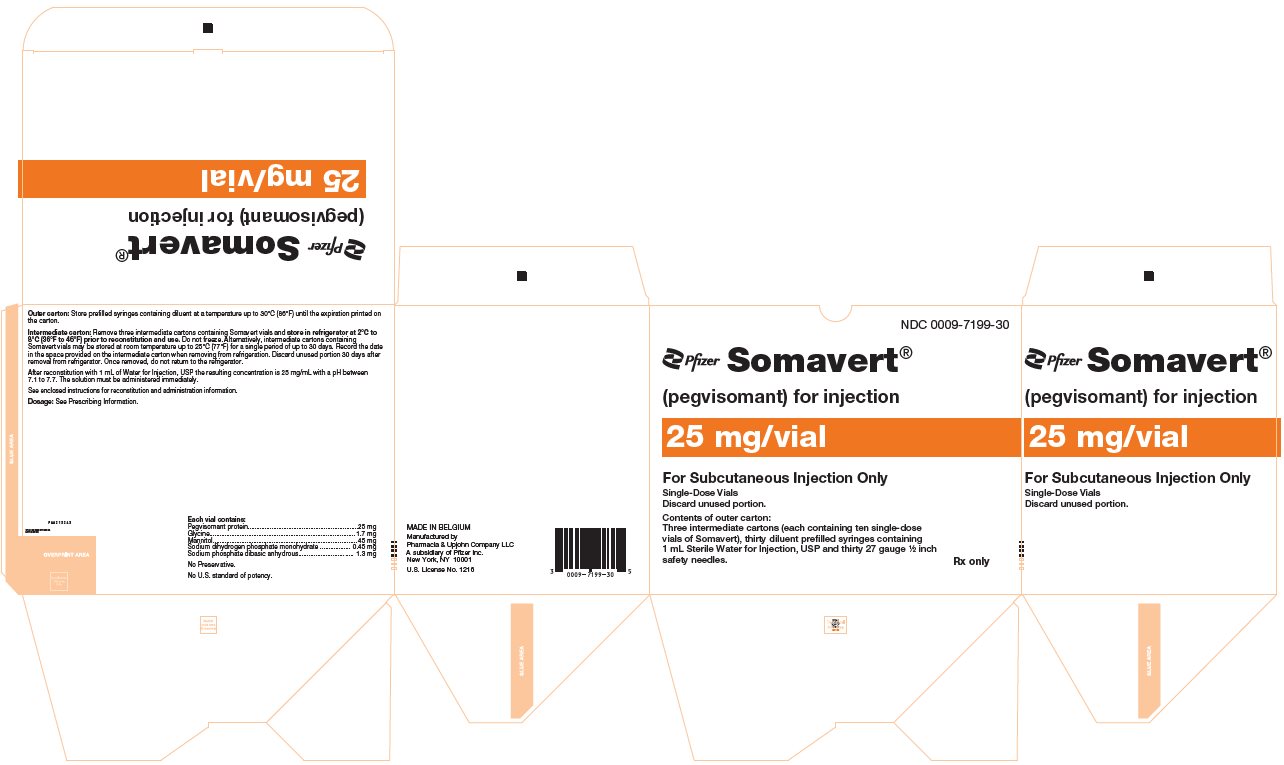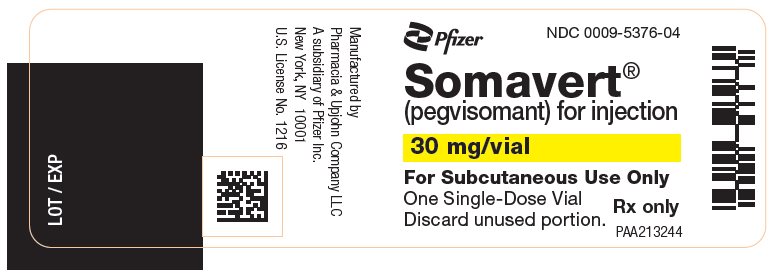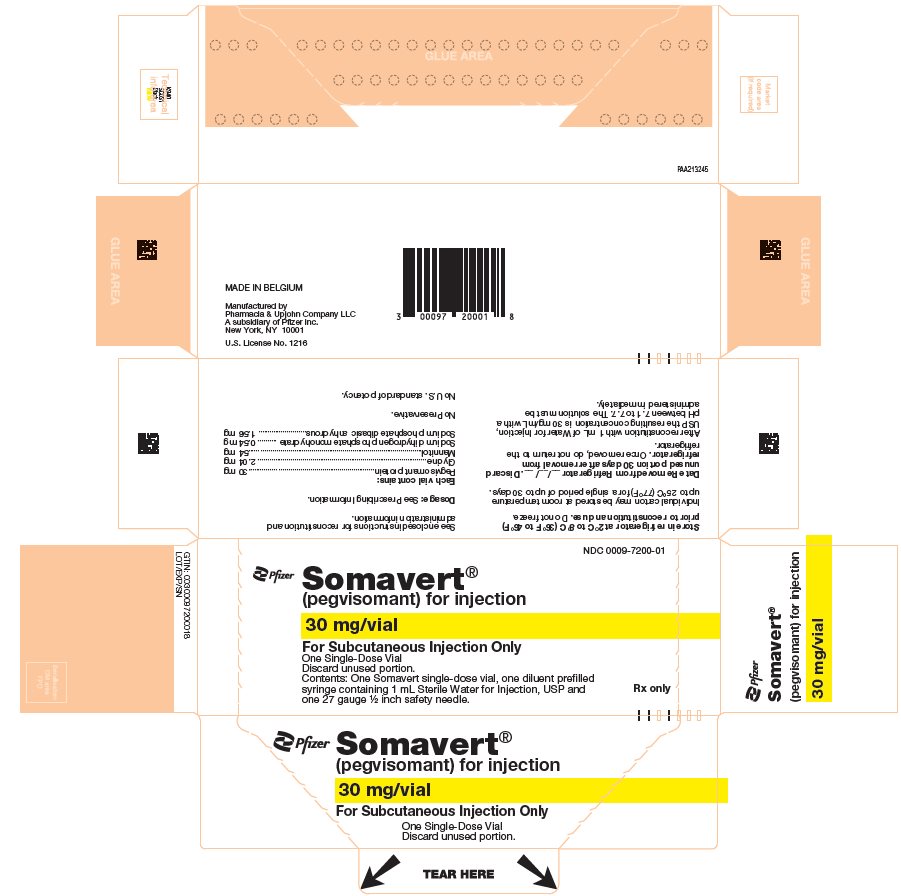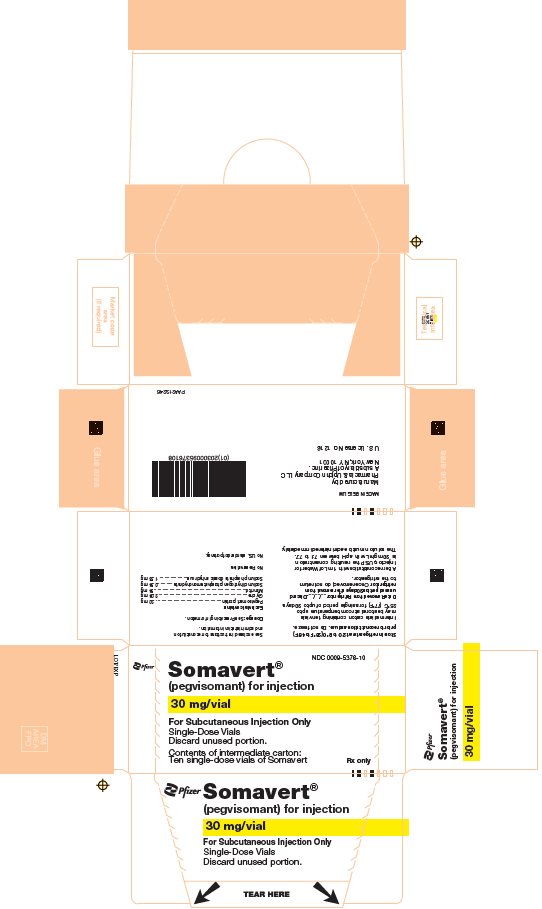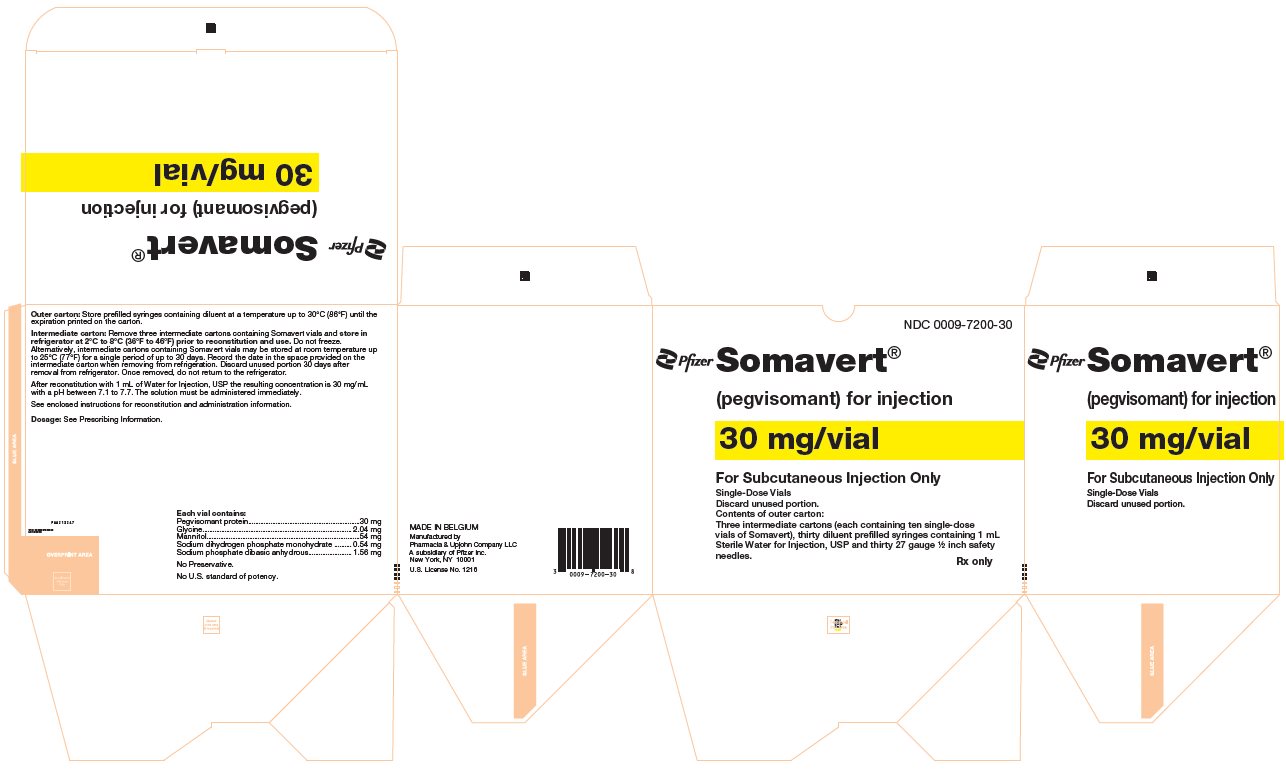 DRUG LABEL: SOMAVERT
NDC: 0009-7166 | Form: KIT | Route: SUBCUTANEOUS
Manufacturer: Pharmacia & Upjohn Company LLC
Category: prescription | Type: HUMAN PRESCRIPTION DRUG LABEL
Date: 20251218

ACTIVE INGREDIENTS: PEGVISOMANT 10 mg/1 mL
INACTIVE INGREDIENTS: GLYCINE 1.36 mg/1 mL; MANNITOL 36 mg/1 mL; SODIUM PHOSPHATE, DIBASIC, ANHYDROUS 1.04 mg/1 mL; SODIUM PHOSPHATE, MONOBASIC, MONOHYDRATE 0.36 mg/1 mL; WATER 1 mL/1 mL

HIGHLIGHTS OF PRESCRIBING INFORMATION

These highlights do not include all the information needed to use SOMAVERT safely and effectively. See full prescribing information for SOMAVERT.
SOMAVERT (pegvisomant) for injection, for subcutaneous use
Initial U.S. Approval: 2003

1 INDICATIONS AND USAGE

SOMAVERT is a growth hormone receptor antagonist indicated for the treatment of acromegaly in patients who have had an inadequate response to surgery or radiation therapy, or for whom these therapies are not appropriate. The goal of treatment is to normalize serum insulin-like growth factor-1 (IGF-1) levels. (1)

2 DOSAGE AND ADMINISTRATION

- Administer a 40 mg loading dose subcutaneously under physician supervision. (2.1)
- After proper injection instruction, on day after loading dose, patients or caregivers begin daily subcutaneous injections of 10 mg. (2.1)
- Adjust dosage in 5 mg increments or decrements until serum IGF-1 concentrations are maintained within age-adjusted normal range. Do not adjust dosage based on growth hormone (GH) levels or signs or symptoms of acromegaly. (2.1)
- Dosage range is 10 mg to 30 mg once daily. (2.1)
- Perform liver tests prior to first dosage and if greater than 3 times upper limit of normal should work-up prior to SOMAVERT administration. (2.2)
- Follow reconstitution and injection procedures. (2.3, 2.4)

3 DOSAGE FORMS AND STRENGTHS

For injection: 10 mg, 15 mg, 20 mg, 25 mg or 30 mg lyophilized powder in a single-dose vial for reconstitution supplied with a prefilled syringe containing 1 mL of diluent (Sterile Water for Injection, USP). (3)

4 CONTRAINDICATIONS

None. (4)

5 WARNINGS AND PRECAUTIONS

- Hypoglycemia: Monitor blood glucose in patients with diabetes mellitus and reduce anti-diabetic drug therapy as necessary. (5.1)
- Liver Toxicity: Should have more frequent liver tests and/or discontinue SOMAVERT. (5.2)
- Systemic Hypersensitivity: Monitor closely when re-initiating SOMAVERT in patients with systemic hypersensitivity. (5.5)

6 ADVERSE REACTIONS

Most common reported adverse reactions (>6%) are infection, pain, nausea, diarrhea, abnormal liver tests, flu syndrome, injection site reaction. (6)
To report SUSPECTED ADVERSE REACTIONS, contact Pfizer Inc. at 1-800-438-1985 or FDA at 1-800-FDA-1088 or www.fda.gov/medwatch.

7 DRUG INTERACTIONS

- Insulin and/or Oral hypoglycemic Agents: Patients with acromegaly and with diabetes mellitus may require careful monitoring and dose reductions of insulin and/or oral hypoglycemic agents. (5.2, 7.1)
- Opioids: Patients on opioids may need higher SOMAVERT doses to achieve appropriate IGF-1 suppression. (7.2)

8 USE IN SPECIFIC POPULATIONS

Females and Males of Reproductive Potential: Advise premenopausal females of the potential for an unintended pregnancy. (8.3)

FULL PRESCRIBING INFORMATION

1 INDICATIONS AND USAGE

SOMAVERT is indicated for the treatment of acromegaly in patients who have had an inadequate response to surgery or radiation therapy, or for whom these therapies are not appropriate. The goal of treatment is to normalize serum insulin-like growth factor-1 (IGF-1) levels.

2 DOSAGE AND ADMINISTRATION

2.1 Dosage Information

The recommended loading dose of SOMAVERT is 40 mg given subcutaneously, under healthcare provider supervision. Provide proper training in subcutaneous injection technique to patients or their caregivers so they can receive once daily subcutaneous injections. On the next day following the loading dose, instruct patients or their caregivers to begin daily subcutaneous injections of 10 mg of SOMAVERT.

Titrate the dosage to normalize serum IGF-1 concentrations (serum IGF-1 concentrations should be measured every four to six weeks). The dosage should not be based on growth hormone (GH) concentrations or signs and symptoms of acromegaly. It is unknown whether patients who remain symptomatic while achieving normalized IGF-1 concentrations would benefit from increased SOMAVERT dosage.

- Increase the dosage by 5 mg increments every 4–6 weeks if IGF-1 concentrations are elevated.
- Decrease the dosage by 5 mg decrements every 4–6 weeks if IGF-1 concentrations are below the normal range.
- IGF-1 levels should also be monitored when a SOMAVERT dose given in multiple injections is converted to a single daily injection [see Clinical Pharmacology (12)].

The recommended dosage range is between 10 mg to 30 mg given subcutaneously once daily and the maximum daily dosage is 30 mg given subcutaneously once daily.

2.2 Assess Liver Tests Prior to Initiation of SOMAVERT

Prior to the start of SOMAVERT, patients should have an assessment of baseline levels of liver tests [serum alanine aminotransferase (ALT), aspartate aminotransferase (AST), serum total bilirubin (TBIL), and alkaline phosphatase (ALP)]. For recommendations regarding initiation of SOMAVERT based on baseline liver tests and recommendations for monitoring of liver tests while on SOMAVERT, refer to Table 1 in Warning and Precautions (5.2).

2.3 Loading Dose Injection Procedure

The following instructions are for the healthcare provider to reconstitute and prepare the 40 mg loading dose. The healthcare provider will need to reconstitute 2 vials of lyophilized powder of SOMAVERT each containing 20 mg of pegvisomant with supplied diluent [two vials of lyophilized powder and two syringes containing 1 mL of diluent (Sterile Water for Injection, USP) will be needed for the 40 mg loading dose]. The healthcare provider will also need to inject the reconstituted SOMAVERT solution twice into the patient's upper arm, upper thigh, abdomen, or buttocks (each injection in a different area).

a) Before administering the loading dose, remove 1 vial of lyophilized powder of SOMAVERT containing 20 mg of pegvisomant and one syringe containing 1 mL of diluent from the refrigerator, if refrigerated, about 10 minutes prior to the planned injection time.
b) Reconstitute the first 20 mg vial of lyophilized powder of SOMAVERT containing 20 mg of pegvisomant with diluent. When using the diluent in the syringe, inject the contents of the syringe slowly onto the sides of the vial containing lyophilized powder of SOMAVERT. Do not inject the diluent directly on the powder.
c) Do not invert the vial or shake the solution as this may cause denaturation of the pegvisomant protein. Slowly swirl the solution to ensure that all of the lyophilized powder has gone into solution. If foaming of the reconstituted SOMAVERT solution is seen, the solution is likely damaged and therefore inappropriate to inject.
d) Visually inspect the reconstituted SOMAVERT solution for particulate matter and discoloration prior to administration. The reconstituted solution should be clear. If the solution is cloudy, do not use it. Once reconstituted, the solution will contain 20 mg of pegvisomant in 1 mL of solution.
e) Withdraw the 1 mL reconstituted SOMAVERT solution. The solution must be administered immediately after reconstitution.
f) Inject the first reconstituted SOMAVERT solution (20 mg/mL) subcutaneously into the patient's upper arm, upper thigh, abdomen, or buttocks using a 90-degree angle.
g) Repeat steps (a) to (e) to reconstitute the second SOMAVERT dose of 20mg.
h) Finally, inject the second reconstituted SOMAVERT solution (20 mg/mL) subcutaneously into the patient's upper arm, upper thigh, abdomen, or buttocks using a 90-degree angle (different area than the first injection).

2.4 Maintenance Dose Injection Procedure

For patient or caregiver instructions for reconstitution and administration of daily doses (10 mg to 30 mg), see the Patient's Instructions for Use.

a) Before administering the dose, remove 1 vial of lyophilized powder of SOMAVERT containing 10 mg, 15 mg, 20 mg, 25 mg or 30 mg of pegvisomant and one syringe containing 1 mL of diluent from the refrigerator, if refrigerated, about 10 minutes prior to the planned injection time.
b) Reconstitute the lyophilized powder of SOMAVERT with diluent. When using the diluent in the 2.25 mL syringe, inject the contents of the syringe slowly onto the sides of the vial containing lyophilized powder of SOMAVERT. Do not inject the diluent directly on the powder.
c) Do not invert the vial or shake the solution as this may cause denaturation of the pegvisomant protein. Slowly swirl the solution to ensure that all of the lyophilized powder has gone into solution. If foaming of the reconstituted SOMAVERT solution is seen, the solution is likely damaged and therefore inappropriate to inject.
d) Visually inspect the reconstituted SOMAVERT solution for particulate matter and discoloration prior to administration. The reconstituted solution should be clear. If the solution is cloudy, do not use it. Once reconstituted, the solution will contain 10 mg, 15 mg, 20 mg, 25 mg or 30 mg of pegvisomant in 1 mL of solution.
e) Withdraw the 1 mL reconstituted SOMAVERT solution. The solution must be administered immediately after reconstitution.
f) Inject the reconstituted SOMAVERT solution subcutaneously into the upper arm, upper thigh, abdomen, or buttocks using a 90-degree angle.

3 DOSAGE FORMS AND STRENGTHS

For injection: 10 mg, 15 mg, 20 mg, 25 mg or 30 mg white lyophilized powder in a single-dose vial for reconstitution supplied with a prefilled syringe containing 1 mL of diluent (Sterile Water for Injection, USP).

4 CONTRAINDICATIONS

None.

5 WARNINGS AND PRECAUTIONS

5.1 Hypoglycemia Associated With GH Lowering in Patients With Diabetes Mellitus

GH opposes the effects of insulin on carbohydrate metabolism by decreasing insulin sensitivity; thus, glucose tolerance may improve in some patients treated with SOMAVERT. Patients should be carefully monitored and doses of anti-diabetic drugs reduced as necessary to avoid hypoglycemia in patients with diabetes mellitus.

5.2 Liver Toxicity

Baseline serum alanine aminotransferase (ALT), aspartate aminotransferase (AST), serum total bilirubin (TBIL), and alkaline phosphatase (ALP) levels should be obtained prior to initiating therapy with SOMAVERT. Table 1 lists recommendations regarding initiation of treatment with SOMAVERT, based on the results of these liver tests (LTs).

Asymptomatic, transient elevations in transaminases up to 15 times ULN have been observed in <2% of subjects among two open-label trials (with a total of 147 patients). These reports were not associated with an increase in bilirubin. Transaminase elevations normalized with time, most often after suspending treatment. Postmarketing reports have identified elevations in serum hepatic transaminases up to greater than 20 times ULN associated with elevation in total bilirubin greater than 2 times ULN. In many of these cases, discontinuation of SOMAVERT therapy resulted in improvement or resolution of hepatic laboratory abnormalities.

SOMAVERT should be used in accordance with the information presented in Table 2 with respect to liver test abnormalities while on SOMAVERT treatment.

Table 1. Recommendations of Initiating SOMAVERT Based on Baseline LTs and Periodic Monitoring of LTs During SOMAVERT Treatment
Baseline LT Levels | Recommendations
Normal | - May treat with SOMAVERT. - Monitor LTs at monthly intervals during the first 6 months of treatment, quarterly for the next 6 months and then bi-annually for the next year.
Elevated, but less than or equal to 3 times ULN | May treat with SOMAVERT; however, monitor LTs monthly for at least one year after initiation of therapy and then bi-annually for the next year.
Greater than 3 times ULN | - Do not treat with SOMAVERT until a comprehensive workup establishes the cause of the patient's liver dysfunction. - Determine if cholelithiasis or choledocholithiasis is present, particularly in patients with a history of prior therapy with somatostatin analogs. - Based on the workup, consider initiation of therapy with SOMAVERT. - If the decision is to treat, LTs and clinical symptoms should be monitored very closely.

If a patient develops LT elevations, or any other signs or symptoms of liver dysfunction while receiving SOMAVERT, the following patient management is recommended (Table 2).

Table 2. Clinical Recommendations Based on Liver Test Results While on SOMAVERT

LT Levels and Clinical Signs/Symptoms | Recommendations
Greater than or equal to 3 but less than 5 times ULN (without signs/symptoms of hepatitis or other liver injury, or increase in serum TBIL) | - May continue therapy with SOMAVERT. However, monitor LTs weekly to determine if further increases occur (see below). - Perform a comprehensive hepatic workup to discern if an alternative cause of liver dysfunction is present.
At least 5 times ULN, or transaminase elevations at least 3 times ULN associated with any increase in serum TBIL (with or without signs/symptoms of hepatitis or other liver injury) | - Discontinue SOMAVERT immediately. - Perform a comprehensive hepatic workup, including serial LTs, to determine if and when serum levels return to normal. - If LTs normalize (regardless of whether an alternative cause of the liver dysfunction is discovered), consider cautious re-initiation of therapy with SOMAVERT, with frequent LT monitoring.
Signs or symptoms suggestive of hepatitis or other liver injury (e.g., jaundice, bilirubinuria, fatigue, nausea, vomiting, right upper quadrant pain, ascites, unexplained edema, easy bruisability) | - Immediately perform a comprehensive hepatic workup. - If liver injury is confirmed, SOMAVERT should be discontinued.

5.3 Cross-Reactivity With GH Assays

SOMAVERT has significant structural similarity to growth hormone (GH) which causes it to cross-react in commercially available GH assays. Since serum concentrations of therapeutically effective doses of SOMAVERT are generally 100 to 1000 times higher than the actual serum GH concentrations seen in patients with acromegaly, measurements of serum GH concentrations will appear falsely elevated.

5.4 Lipohypertrophy

There have been cases of lipohypertrophy in patients treated with SOMAVERT. In a double-blind, 12-week, placebo-controlled study, there was one case (1.3%) of injection site lipohypertrophy reported in a subject receiving 10 mg/day. The subject recovered while on treatment. Among two open-label trials (with a total of 147 patients), there were two subjects, both receiving 10 mg/day, who developed lipohypertrophy. One case recovered while on treatment, and one case resulted in a discontinuation of treatment. Injection sites should be rotated daily to help prevent lipohypertrophy (different area than the last injection).

5.5 Systemic Hypersensitivity

In patients with systemic hypersensitivity reactions, caution and close monitoring should be exercised when re-initiating SOMAVERT therapy [see Adverse Reactions (6.2)].

6 ADVERSE REACTIONS

Clinically significant adverse reactions that appear in other section of the labeling include:

- Hypoglycemia Associated with GH Lowering in Patients with Diabetes Mellitus [see Warnings and Precautions (5.1)]
- Liver Toxicity [see Warnings and Precautions (5.2)]
- Cross-Reactivity with GH Assays [see Warnings and Precautions (5.3)]
- Lipohypertrophy [see Warnings and Precautions (5.4)]
- Systemic Hypersensitivity [see Warnings and Precautions (5.5)]

Elevations of serum concentrations of ALT and AST greater than ten times the ULN were reported in two patients (0.8%) exposed to SOMAVERT in pre-approval clinical studies. One patient was rechallenged with SOMAVERT, and the recurrence of elevated transaminase levels suggested a probable causal relationship between administration of the drug and the elevation in liver enzymes. A liver biopsy performed on the second patient was consistent with chronic hepatitis of unknown etiology. In both patients, the transaminase elevations normalized after discontinuation of the drug.

Elevations in ALT and AST levels were not associated with increased levels of TBIL and ALP, with the exception of two patients with minimal associated increases in ALP levels (i.e., less than 3 times ULN). The transaminase elevations did not appear to be related to the dose of SOMAVERT administered, generally occurred within 4 to 12 weeks of initiation of therapy, and were not associated with any identifiable biochemical, phenotypic, or genetic predictors.

6.1 Clinical Trials Experience

Because clinical trials are conducted under widely varying conditions, adverse reaction rates observed in the clinical trials of a drug cannot be directly compared to rates in the clinical trials of another drug and may not reflect the rates observed in practice.

In a 12-week randomized, placebo-controlled, double-blind, fixed-dose study of SOMAVERT in subjects with acromegaly, 32 subjects received placebo and 80 subjects received SOMAVERT once daily [see Clinical Studies (14)]. A total of 108 subjects (30 placebo, 78 SOMAVERT) completed 12 weeks of study treatment.

Overall, eight patients with acromegaly (5.3%) withdrew from pre-marketing clinical studies because of adverse events, including two patients with marked transaminase elevations, one patient with lipohypertrophy at the injection sites, and one patient with substantial weight gain. Most adverse events did not appear to be dose-dependent. Table 3 shows the incidence of adverse events that were reported in at least two patients treated with SOMAVERT and at frequencies greater than placebo during the 12-week, placebo-controlled study.

Table 3. Adverse Reactions in a 12-week Placebo-Controlled Study in Patients with Acromegaly [Table includes only those events that were reported in at least 2 patients and at a higher incidence in patients treated with SOMAVERT than in patients treated with placebo.]
 | Placebo n=32 | SOMAVERT
 | Placebo n=32 | 10 mg/day n=26 | 15 mg/day n=26 | 20 mg/day N=28
Infection [The 6 events coded as "infection" in the group treated with SOMAVERT 10 mg were reported as cold symptoms (3), upper respiratory infection (1), blister (1), and ear infection (1). The 2 events in the placebo group were reported as cold symptoms (1) and chest infection (1).] | 2 (6%) | 6 (23%) | 0 | 0
Pain | 2 (6%) | 2 (8%) | 1 (4%) | 4 (14%)
Nausea | 1 (3%) | 0 | 2 (8%) | 4 (14%)
Diarrhea | 1 (3%) | 1 (4%) | 0 | 4 (14%)
Abnormal liver function tests | 1 (3%) | 3 (12%) | 1 (4%) | 1 (4%)
Flu syndrome | 0 | 1 (4%) | 3 (12%) | 2 (7%)
Injection site reaction | 0 | 2 (8%) | 1 (4%) | 3 (11%)
Dizziness | 2 (6%) | 2 (8%) | 1 (4%) | 1 (4%)
Accidental injury | 1 (3%) | 2 (8%) | 1 (4%) | 0
Back pain | 1 (3%) | 2 (8%) | 0 | 1 (4%)
Sinusitis | 1 (3%) | 2 (8%) | 0 | 1 (4%)
Chest pain | 0 | 1 (4%) | 2 (8%) | 0
Peripheral edema | 0 | 2 (8%) | 0 | 1 (4%)
Hypertension | 0 | 0 | 2 (8%) | 0
Paresthesia | 2 (6%) | 0 | 0 | 2 (7%)

6.2 Postmarketing Experience

Adverse Reactions from Postmarketing Spontaneous Reports

The following adverse reactions have been identified during post-approval use of SOMAVERT. Because these reactions are reported voluntarily from a population of uncertain size, it is not always possible to reliably estimate their frequency or establish a causal relationship to drug exposure.

Systemic hypersensitivity reactions including anaphylactic reactions, laryngospasm, angioedema, generalized skin reactions (rash, erythema, pruritus, urticaria) have been reported in post-marketing use. Some patients required hospitalization. Symptoms did not re-occur in all patients after re-challenge [see Warnings and Precautions (5.5)].

Adverse Reactions from an Observational Study

ACROSTUDY was an international observational registry that captured long term safety data in 2221 patients with acromegaly treated with SOMAVERT for a mean treatment duration of 8.5 years. Patients could also receive other therapy for acromegaly during the registry period. Treatment dose and schedule were at the discretion of each treating healthcare provider. Although safety monitoring as per the recommended schedule was mandatory, not all assessments were performed at all time points for every patient. Because of this, comparison of rates of adverse events to those in the original clinical trial is not appropriate. Of the 1327 patients who had a normal AST and ALT at baseline, 20 (1.5%) patients had elevated tests >3-5 times ULN, and 22 (1.7%) patients had elevated tests >5 times ULN. Lipohypertrophy was reported in 35 (1.6%) patients. Of the 1795 patients who had a MRI reported at baseline and at least once during follow up in the study, MRI results showed that 128 (7.1%) were reported to have an increase, 310 (17.3%) were reported to have a decrease, 81 (4.5%) had both increase and decrease, and 1276 (71.1%) had no change.

7 DRUG INTERACTIONS

7.1 Insulin and/or Oral Hypoglycemic Agents

After initiation of SOMAVERT, patients with acromegaly and diabetes mellitus treated with insulin and/or oral hypoglycemic agents may require dose reductions of insulin and/or oral hypoglycemic agents [see Warnings and Precautions (5.1)].

7.2 Opioids

In clinical studies, patients taking opioids often needed higher SOMAVERT doses to normalize IGF-1 concentrations compared with patients not receiving opioids. The mechanism of this interaction is not known.

8 USE IN SPECIFIC POPULATIONS

8.1 Pregnancy

Risk Summary

Postmarketing reports of SOMAVERT use in pregnant women are insufficient to establish a drug-associated risk for major birth defects, miscarriage or adverse maternal or fetal outcomes. Acromegaly may improve during pregnancy (see Clinical Considerations). In animal reproduction studies, fetotoxicity was observed at a dose that was 6 times the maximum recommended human dose based on body surface area following subcutaneous administration of pegvisomant during organogenesis or during the preimplantation period (see Data).

The estimated background risk of major birth defects and miscarriage for the indicated population is unknown. In the U.S. general population, the estimated background risk of major birth defects and miscarriage in clinically recognized pregnancies is 2–4% and 15–20%, respectively.

Clinical Considerations

Disease-associated maternal and/or embryofetal risk

Published data from case reports, case series, and a small interventional study in pregnant women with acromegaly have demonstrated that acromegaly may improve or stabilize without treatment during pregnancy, particularly if acromegaly is treated before pregnancy. In rare cases, acromegaly may worsen during pregnancy. Since IGF-1 levels may change physiologically during pregnancy and interpreting IGF-1 and growth hormone levels in pregnant women with acromegaly may be unreliable, clinical monitoring is recommended.

Data

Animal Data

The effects of pegvisomant on early embryonic development and embryo-fetal development were evaluated in two separate studies, which were conducted in pregnant rabbits with pegvisomant at subcutaneous doses of 1, 3, and 10 mg/kg/day. There was no evidence of teratogenic effects associated with pegvisomant administration during organogenesis. At the 10-mg/kg/day dose (6 times the maximum human therapeutic dose based on body surface area), a reproducible, slight increase in post-implantation loss was observed in both studies.

8.2 Lactation

Risk Summary

Limited information from a case report in published literature reported that the level of pegvisomant in human milk was below the level of detection. There is no information available on the effects of the drug on the breastfed infant or the effects of the drug on milk production. The developmental and health benefits of breastfeeding should be considered along with the mother's clinical need for SOMAVERT and any potential adverse effects on the breastfed child from SOMAVERT or from the underlying maternal condition.

8.3 Females and Males of Reproductive Potential

Discuss the potential for unintended pregnancy with premenopausal women as the therapeutic benefits of a reduction in growth hormone (GH) levels and normalization of insulin-like growth factor 1 (IGF-1) concentration in acromegalic females treated with pegvisomant may lead to improved fertility.

8.4 Pediatric Use

The safety and effectiveness of SOMAVERT in pediatric patients have not been established.

8.5 Geriatric Use

Clinical studies of SOMAVERT did not include sufficient numbers of patients aged 65 and over to determine whether they respond differently from younger patients. In general, dose selection for an elderly patient should be cautious, usually starting at the low end of the dosing range, reflecting the greater frequency of decreased hepatic, renal, or cardiac function, and of concomitant disease or other drug therapy.

8.6 Renal Impairment

SOMAVERT was not studied in patients with renal impairment and the safety and efficacy in these patients is not known.

10 OVERDOSAGE

In one reported incident of acute overdose with SOMAVERT during pre-marketing clinical studies, a patient self-administered 80 mg/day (2.7 times the maximum recommended maintenance dosage) for seven days. The patient experienced a slight increase in fatigue, had no other complaints, and demonstrated no significant clinical laboratory abnormalities.

In cases of overdose, administration of SOMAVERT should be discontinued and not resumed until IGF-1 levels return to within or above the normal range.

11 DESCRIPTION

Pegvisomant is an analog of human growth hormone (GH) of recombinant DNA origin that acts as a GH receptor antagonist.

It contains 191 amino acid residues. The molecular weight of pegvisomant is 22 kDa. The molecular weight of the PEG portion of pegvisomant is approximately 5 kDa. The predominant molecular weights of pegvisomant are thus approximately 42, 47, and 52 kDa. The schematic shows the amino acid sequence of the pegvisomant protein (PEG polymers are shown attached to the 5 most probable attachment sites). Pegvisomant is synthesized by a specific strain of Escherichia coli bacteria that has been genetically modified by the addition of a plasmid that carries a gene for GH receptor antagonist.

Stippled residues indicate PEG attachment sites (Phe1, Lys38, Lys41, Lys70, Lys115, Lys120, Lys140, Lys145, Lys158)

Shown below are the amino acid substitutions in pegvisomant, relative to human GH.

hGH | Pegvisomant
His18 | Asp18
Ala21 | Asn21
Gly120 | Lys120
Arg167 | Asn167
Lys168 | Ala168
Asp171 | Ser171
Lys172 | Arg172
Glu174 | Ser174
Ile179 | Thr179

SOMAVERT (pegvisomant) for injection is a sterile, white lyophilized powder intended for subcutaneous injection after reconstitution. SOMAVERT is supplied in packages that include a single-dose prefilled syringe containing 1 mL of Sterile Water for Injection, USP, that is a sterile, nonpyrogenic preparation of water for injection that contains no bacteriostat, antimicrobial agent, or added buffer, to be used as a diluent.

SOMAVERT is available in single-dose sterile vials containing 10 mg, 15 mg, 20 mg, 25 mg or 30 mg of pegvisomant. SOMAVERT 10 mg, 15 mg, and 20 mg vials also contain glycine (1.36 mg), mannitol (36 mg), sodium dihydrogen phosphate monohydrate (0.36 mg), and sodium phosphate dibasic anhydrous (1.04 mg). After reconstitution with 1 mL of Water for Injection, USP, the resulting concentration is 10 mg/mL, 15 mg/mL and 20 mg/mL, respectively, with a pH of 7.1 – 7.7.

SOMAVERT 25 mg vial also contains glycine (1.7 mg), mannitol (45 mg), sodium dihydrogen phosphate monohydrate (0.45 mg), and sodium phosphate dibasic anhydrous (1.3 mg). After reconstitution with 1 mL of Water for Injection, USP, the resulting concentration is 25 mg/mL with a pH of 7.1 – 7.7.

SOMAVERT 30 mg vial also contains glycine (2.04 mg), mannitol (54 mg), sodium dihydrogen phosphate monohydrate (0.54 mg), and sodium phosphate dibasic anhydrous (1.56 mg). After reconstitution with 1 mL of Water for Injection, USP, the resulting concentration is 30 mg/mL with a pH of 7.1 – 7.7.

12 CLINICAL PHARMACOLOGY

12.1 Mechanism of Action

Pegvisomant selectively binds to growth hormone (GH) receptors on cell surfaces, where it blocks the binding of endogenous GH, and thus interferes with GH signal transduction.

Inhibition of GH action results in decreased serum concentrations of IGF-1, as well as other GH-responsive serum proteins such as free IGF-1, the acid-labile subunit of IGF-1 (ALS), and insulin-like growth factor binding protein-3 (IGFBP-3).

12.2 Pharmacodynamics

Pegvisomant binds selectively to the GH receptor, and does not cross-react with 19 other cytokine receptors tested, including prolactin. Pegvisomant leads to decreased serum concentrations of IGF-1, free IGF-1, ALS, and IGFBP-3 [see Clinical Studies (14, Figure 1)].

12.3 Pharmacokinetics

Absorption: Following subcutaneous administration, peak serum pegvisomant concentrations are not generally attained until 33 to 77 hours after administration. The mean extent of absorption of a 20-mg subcutaneous dose was 57%, relative to a 10-mg intravenous dose.

Distribution: The mean apparent volume of distribution of pegvisomant is 7 L (12% coefficient of variation), suggesting that pegvisomant does not distribute extensively into tissues. After a single subcutaneous administration, exposure (Cmax, AUC) to pegvisomant increases disproportionately with increasing dose. Mean ± SEM serum pegvisomant concentrations after 12 weeks of therapy with daily doses of 10, 15, and 20 mg were 6600 ± 1330; 16,000 ± 2200; and 27,000 ± 3100 ng/mL, respectively.

The relative bioavailability of 1 × 30 mg pegvisomant was compared to 2 × 15 mg pegvisomant in a single-dose study. The AUCinf and Cmax of pegvisomant when administered as one injection of 30 mg strength was approximately 6% and 4% greater, respectively, as compared to when administered as two injections of 15 mg strengths.

Metabolism and Elimination: The pegvisomant molecule contains covalently bound polyethylene glycol polymers in order to reduce the clearance rate. Clearance of pegvisomant following multiple doses is lower than seen following a single-dose. The mean total body systemic clearance of pegvisomant following multiple doses is estimated to range between 36 to 28 mL/h for subcutaneous doses ranging from 10 to 20 mg/day, respectively. Clearance of pegvisomant was found to increase with body weight. Pegvisomant is eliminated from serum with a mean half-life estimates ranging from 60 to 138 hours following either single or multiple doses. Less than 1% of administered drug is recovered in the urine over 96 hours. The elimination route of pegvisomant has not been studied in humans.

Drug Interaction Studies

In clinical studies, patients on opioids often needed higher serum pegvisomant concentrations to achieve appropriate IGF-1 suppression compared with patients not receiving opioids. The mechanism of this interaction is not known [see Drug Interactions (7.2)].

Specific Populations

No pharmacokinetic studies have been conducted in patients with renal impairment, patients with hepatic impairment, geriatric patients, or pediatric patients and the effects of race on the pharmacokinetics of pegvisomant has not been studied. No gender effect on the pharmacokinetics of pegvisomant was found in a population pharmacokinetic analysis.

12.6 Immunogenicity

The observed incidence of anti-drug antibodies is highly dependent on the sensitivity and specificity of the assay. Differences in assay methods preclude meaningful comparisons of the incidence of anti-drug antibodies in the studies described below with the incidence of anti-drug antibodies in other studies, including those of SOMAVERT or other growth hormone analogs.

In pre-marketing clinical studies, approximately 17% of the SOMAVERT-treated patients developed low titer, non‑neutralizing anti-GH antibodies. Although the presence of these antibodies did not appear to impact the efficacy of SOMAVERT, the long term clinical significance of these antibodies is not known. No assay for anti-pegvisomant antibodies is commercially available for patients receiving SOMAVERT.

The data above reflect the percentage of patients whose test results were considered positive for antibodies to SOMAVERT. The detection of antibody formation is highly dependent on the sensitivity and specificity of the assay. Additionally, the observed incidence of antibody positivity in an assay may be influenced by several factors including sample handling, timing of sample collection, concomitant medications, and underlying disease. For these reasons, comparison of the incidence of antibodies to SOMAVERT with the incidence of antibodies to other products may be misleading.

13 NONCLINICAL TOXICOLOGY

13.1 Carcinogenesis, Mutagenesis, Impairment of Fertility

Carcinogenesis

Pegvisomant was administered subcutaneously to rats daily for 2 years at doses of 2, 8, and 20 mg/kg (about 2, 9, and 22-fold a single 30 mg dose in humans on an AUC basis). Long term treatment with pegvisomant at 8 and 20 mg/kg caused an increase in malignant fibrous histiocytoma at injection sites in males. Injection site tumors were not seen in female rats at the same doses. The increased incidence of injection site tumors was most probably caused by irritation and the high sensitivity of the rat to repeated subcutaneous injections.

Mutagenesis

Pegvisomant did not cause genetic damage in standard in vitro assays (bacterial mutation, human lymphocyte chromosome aberration).

Impairment of Fertility

Fertility studies have not been conducted with pegvisomant.

14 CLINICAL STUDIES

A total of one hundred twelve patients (63 men and 49 women) with acromegaly participated in a 12-week, randomized, double-blind, multi-center study comparing placebo and SOMAVERT. The mean ±SD age was 48±14 years, and the mean duration of acromegaly was 8±8 years. Ninety three had undergone previous pituitary surgery, of which 57 had also been treated with conventional radiation therapy. Six patients had undergone irradiation without surgery, nine had received only drug therapy, and four had received no previous therapy. At study start, the mean ± SD time since the subjects' last surgery and/or irradiation therapy, respectively, was 6.8 ± 0.93 years (n=63) and 5.6 ± 0.57 years (n=93).

Subjects were qualified for enrollment if their serum IGF-1, drawn after the required drug washout period, was ≥1.3 times the upper limit of the age-adjusted normal range. They were randomly assigned at the baseline visit to one of four treatment groups: placebo (n=32), 10 mg/day (n=26), 15 mg/day (n= 26), or 20 mg/day (n=28) of SOMAVERT subcutaneously IGF-1. The primary efficacy endpoint was IGF-1 percent change in IGF-1 concentrations from baseline to week 12. The three groups that received SOMAVERT showed statistically significant (p<0.01) reductions in serum levels of IGF-1 compared with the placebo group (Table 4).

Table 4. Mean Percent Change from Baseline in IGF-1 at Week 12 for Intent-to-Treat Population
 | Placebo n=31 | SOMAVERT
 | Placebo n=31 | 10 mg/day n=26 | 15 mg/day n=26 | 20 mg/day n=28
Mean baseline IGF-1 (ng/ml) (SD) | 670 (288) | 627 (251) | 649 (293) | 732 (205)
Mean percent change from baseline in IGF-1 (SD) | -4.0 (17) | -27 (28) | -48 (26) | -63 (21)
SOMAVERT minus Placebo (95% CI for treatment difference) |  | -23 [P<0.01; n=number of patients; SD = standard deviation] (-35, -11) | -44 (-56, -33) | -59 (-68, -49)

There were also reductions in serum levels of free IGF-1, IGFBP-3, and ALS compared with placebo at all post-baseline visits (Figure 1).

Figure 1. Effects of SOMAVERT on Serum Markers (Mean ± Standard Error)

After 12 weeks of treatment, the following percentages of patients had normalized IGF-1 (Figure 2):

Figure 2. Percent of Patients Whose IGF-1 Levels Normalized at Week 12

Table 5 shows the effect of treatment with SOMAVERT on ring size (standard jeweler's sizes converted to a numeric score ranging from 1 to 63), and on signs and symptoms of acromegaly. Each individual score for a sign or symptom of acromegaly (for soft-tissue swelling, arthralgia, headache, perspiration and fatigue) was based on a nine-point ordinal rating scale (0 = absent and 8 = severe and incapacitating), and the total score for signs or symptoms of acromegaly was derived from the sum of the individual scores. Mean baseline scores were as follows: ring size = 47.1; total signs and symptoms = 15.2; soft tissue swelling = 2.5; arthralgia = 3.2; headache = 2.4; perspiration = 3.3; and fatigue = 3.7.

Table 5. Mean Change from Baseline (SD) at Week 12 for Ring Size and Signs and Symptoms of Acromegaly
 | Placebo n=30 | SOMAVERT
 | Placebo n=30 | 10 mg/day n=26 | 15 mg/day n=24–25 | 20 mg/day n=26–27
Ring size | -0.1 (2.3) | -0.8 (1.6) | -1.9 (2.0) | -2.5 (3.3)
Total score for signs and symptoms of acromegaly | 1.3 (6.0) | -2.5 (4.3) | -4.4 (5.9) | -4.7 (4.7)
Soft-tissue swelling | 0.3 (2.3) | -0.7 (1.6) | -1.2 (2.3) | -1.3 (1.3)
Arthralgia | 0.1 (1.8) | -0.3 (1.8) | -0.5 (2.5) | -0.4 (2.1)
Headache | 0.1 (1.7) | -0.4 (1.6) | -0.3 (1.4) | -0.3 (2.0)
Perspiration | 0.1 (1.7) | -0.6 (1.6) | -1.1 (1.3) | -1.7 (1.6)
Fatigue | 0.7 (1.5) | -0.5 (1.4) | -1.3 (1.7) | -1.0 (1.6)

Serum growth hormone (GH) concentrations, as measured by research assays using antibodies that do not cross-react with pegvisomant, rose within two weeks of beginning treatment with SOMAVERT. The largest increase in GH concentration was seen in patients treated with doses of SOMAVERT 20 mg/day. This effect is presumably the result of diminished inhibition of GH secretion as IGF-1 levels fall. As shown in Figure 3, when patients with acromegaly were given a loading dose of SOMAVERT followed by a fixed daily dose, the rise in GH was inversely proportional to the fall in IGF-1 and generally stabilized by week 2. Serum GH concentrations remained stable in patients treated with SOMAVERT for the average of 43 weeks (range, 0–82 weeks).

Figure 3. Percent Change in Serum GH and IGF-1 Concentrations

In the open-label extension to the clinical study, 109 subjects (including 6 new patients) with mean treatment exposure of 42.6 weeks (range 1 day – 82 weeks), 93 (85.3%) subjects had an adverse event, 16 (14.7%) had an SAE, and 4 (3.7%) discontinued due to an AE (headaches, elevated liver function tests, pancreatic cancer, and weight gain). A total of 100 (92.6%) of the 108 subjects with available IGF-1 data had a normal IGF-1 concentration at any visit during the study.

16 HOW SUPPLIED/STORAGE AND HANDLING

SOMAVERT (pegvisomant) for injection is a white lyophilized powder supplied in the following strengths and package configurations:

One Day Package Configuration
Strength | NDC | Description
10 mg per vial | 0009-7166-01 | One single-dose vial with one prefilled syringe containing 1 mL of diluent (Sterile Water for Injection, USP) and a separate 27 -gauge ½ inch safety needle per carton
15 mg per vial | 0009-7168-01 | One single-dose vial with one prefilled syringe containing 1 mL of diluent (Sterile Water for Injection, USP) and a separate 27 -gauge ½ inch safety needle per carton
20 mg per vial | 0009-7188-01 | One single-dose vial with one prefilled syringe containing 1 mL of diluent (Sterile Water for Injection, USP) and a separate 27 -gauge ½ inch safety needle per carton
25 mg per vial | 0009-7199-01 | One single-dose vial with one prefilled syringe containing 1 mL of diluent (Sterile Water for Injection, USP) and a separate 27 -gauge ½ inch safety needle per carton
30 mg per vial | 0009-7200-01 | One single-dose vial with one prefilled syringe containing 1 mL of diluent (Sterile Water for Injection, USP) and a separate 27 -gauge ½ inch safety needle per carton

30-Day Package Configuration
Strength | NDC | Description
10 mg per vial | 0009-7166-30 | Each outer carton contains three intermediate cartons, 30 prefilled syringes containing 1 mL of diluent (Sterile Water for Injection, USP), and 30 separate 27-gauge ½ inch safety needles. Each intermediate carton contains ten single-dose vials of Somavert.
15 mg per vial | 0009-7168-30 | Each outer carton contains three intermediate cartons, 30 prefilled syringes containing 1 mL of diluent (Sterile Water for Injection, USP), and 30 separate 27-gauge ½ inch safety needles. Each intermediate carton contains ten single-dose vials of Somavert.
20 mg per vial | 0009-7188-30 | Each outer carton contains three intermediate cartons, 30 prefilled syringes containing 1 mL of diluent (Sterile Water for Injection, USP), and 30 separate 27-gauge ½ inch safety needles. Each intermediate carton contains ten single-dose vials of Somavert.
25 mg per vial | 0009-7199-30 | Each outer carton contains three intermediate cartons, 30 prefilled syringes containing 1 mL of diluent (Sterile Water for Injection, USP), and 30 separate 27-gauge ½ inch safety needles. Each intermediate carton contains ten single-dose vials of Somavert.
30 mg per vial | 0009-7200-30 | Each outer carton contains three intermediate cartons, 30 prefilled syringes containing 1 mL of diluent (Sterile Water for Injection, USP), and 30 separate 27-gauge ½ inch safety needles. Each intermediate carton contains ten single-dose vials of Somavert.

Storage

Prior to reconstitution:

- The One Day Package of SOMAVERT should be stored in a refrigerator at 2°C to 8°C (36°F to 46°F).
- For the 30-Day Package, remove the three intermediate cartons containing the SOMAVERT vials and store in a refrigerator at 2°C to 8°C (36°F to 46°F).
- For convenience, the One Day Package and intermediate cartons in the 30-Day Package containing the SOMAVERT vial(s), may be stored at room temperature up to 25°C (77°F) for a single period of up to 30 days.
  - In the space provided on the carton, record the date when the carton was removed from the refrigerator and the discard date (30 days after removal from the refrigerator).
  - Once the carton has been stored at room temperature, it should not be placed back into the refrigerator. If not used within 30 days at room temperature, the vial(s) should be discarded.

Discard the SOMAVERT vial(s) after the expiration date printed on the carton or the discard date, whichever is sooner.

The prefilled syringe(s) may be stored at a temperature up to 30°C (86°F) until the expiration date printed on the carton, at which point they should be discarded.

Do not freeze.

17 PATIENT COUNSELING INFORMATION

Advise the patient to read the FDA-approved patient labeling (Patient Information and Instructions for Use).

Inform patients (and/or their caregivers) of the following information to aid in the safe and effective use of SOMAVERT:

- Not to use SOMAVERT if they are allergic to SOMAVERT or anything in it.
- They will need blood testing to check IGF-1 levels and liver tests before and during treatment with SOMAVERT and that the dose of SOMAVERT may be changed based on the results of these tests.
- SOMAVERT has not been studied in pregnant women and instruct them to notify their healthcare provider as soon as they are aware that they are pregnant.
- It is not known whether SOMAVERT is excreted in human milk and instruct them to notify their healthcare provider if they plan to do so.
- Pregnancy: Inform female patients that treatment with SOMAVERT may result in unintended pregnancy [see Females and Males of Reproductive Potential (8.3)].

Advise patients (and/or their caregivers) of the following adverse reactions:

- The most common reported adverse reactions are injection site reaction, elevations of liver tests, pain, nausea, and diarrhea.
- If they have liver test elevations they may need to have more frequent liver tests and/or discontinue SOMAVERT. Instruct patients to immediately discontinue therapy and contact their physician if they become jaundiced.
- GH-secreting tumors may enlarge in people with acromegaly and that these tumors need to be watched carefully and monitored by MRI imaging.
- Thickening under the skin may occur at the injection site that could lead to lumps and that switching sites may prevent or lessen this.
- If they have diabetes mellitus, they may require careful monitoring and dose reductions of insulin and/or oral hypoglycemic agents while on SOMAVERT.
- If they take opioids, they may need higher SOMAVERT doses to achieve appropriate IGF-1 suppression.

Inform patients (and/or their caregivers) about the storage options prior to reconstitution of the product [see How Supplied/Storage and Handling (16)].

Advise patients to follow the directions for reconstitution provided in the Instructions for Use. Include that spraying the diluent directly onto the powder may cause foaming and that shaking may induce denaturation (destruction) of the active ingredient (therefore do not shake).

U.S. License No. 1216

This product's labeling may have been updated. For the most recent prescribing information, please visit www.pfizer.com.

LAB-0782-4.0

PATIENT INFORMATION
SOMAVERT (SOM-ah-vert)
(pegvisomant)
for injection, for subcutaneous use

What is SOMAVERT?
SOMAVERT is a prescription medicine used to treat people who have too much growth hormone (acromegaly). SOMAVERT is used to treat people who are not able to be treated or have not already been helped by surgery or radiation.
It is not known if SOMAVERT is safe and effective in children.

Before you use SOMAVERT, tell your healthcare provider about all of your medical conditions, including if you:

- are allergic to pegvisomant or any of the ingredients in SOMAVERT. Do not take SOMAVERT if you are allergic to pegvisomant or any of the ingredients in SOMAVERT. See the end of this Patient Information leaflet for a complete list of ingredients in SOMAVERT.
- have diabetes.
- have or have had liver problems.
- are pregnant or plan to become pregnant. It is not known if SOMAVERT will harm your unborn baby. Tell your healthcare provider if you become pregnant while using SOMAVERT.
- are breastfeeding or plan to breastfeed. It is not known if SOMAVERT passes into your breast milk. You and your healthcare provider should decide how you will feed your baby if you take SOMAVERT.

Tell your healthcare provider about all the medicines you take, including prescription and over-the-counter medicines, vitamins, and herbal supplements.
SOMAVERT may affect the way other medicines work, and other medicines may affect how SOMAVERT works.
Especially tell your healthcare provider if you take:

- insulin or other medicines used to treat diabetes.
- narcotics (opioid medicines). Your healthcare provider may change your dose of SOMAVERT if you take opioids.

If you are not sure, ask your healthcare provider or pharmacist whether you take these medicines.

How should I use SOMAVERT?

- Read the Instructions for Use at the end of this Patient Information for information about the right way to use SOMAVERT.
- Your healthcare provider should do blood tests to check your liver and insulin-like growth factor-1 (IGF-1) levels before you start and while you use SOMAVERT. Your healthcare provider may need to change your dose of SOMAVERT.
- SOMAVERT is given 1 time each day as an injection under your skin (subcutaneous). Some people may need to give 2 injections for their dose each day. Your healthcare provider will tell you if you need to give 2 injections for your dose.
- Your first injection of SOMAVERT should be given by your healthcare provider.
- Your healthcare provider will teach you or your caregiver how to use SOMAVERT.
- If you use too much SOMAVERT, call your healthcare provider right away.
- If you miss a dose of SOMAVERT, just take the next dose at the regular time. Do not take 2 doses at the same time. If you are not sure about your dosing, ask your healthcare provider.

What are the possible side effects of SOMAVERT?
SOMAVERT may cause serious side effects, including:

- changes in your blood sugar level. Your healthcare provider may change your dose of diabetes medicine while you take SOMAVERT.
- liver problems. Stop injecting SOMAVERT right away and call your healthcare provider if you have any of the following symptoms of liver problems:

- yellowing of your eyes (jaundice)
- dark, amber-colored urine
- feeling very tired (fatigue or exhaustion)
- nausea and vomiting

- pain in your stomach (abdomen)
- generalized swelling
- bruising easily

- skin thickening at your injection site that could lead to lumps (lipohypertrophy)
- allergic reactions. Call your healthcare provider right away if you have any of the following symptoms of a serious allergic reaction:

- swelling of your face, tongue, lips, or throat
- wheezing or trouble breathing
- skin rash, redness, or swelling

- severe itching
- dizziness or fainting

The most common side effects of SOMAVERT include:

- pain
- infection
- nausea
- flu syndrome

- injection site reaction
- diarrhea
- abnormal liver tests. If your liver test results are too high, you may have to have more frequent liver tests

These are not all of the possible side effects of SOMAVERT. For more information, ask your healthcare provider or pharmacist.
Tell your healthcare provider if you have any side effect that bothers you or that does not go away.
Call your doctor for medical advice about side effects. You may report side effects to FDA at 1-800-FDA-1088.

How should I store SOMAVERT?

- Before you mix the SOMAVERT powder and the liquid:
  - Store SOMAVERT in a refrigerator at 36°F to 46°F (2°C to 8°C).
  - The One Day Package and intermediate cartons in the 30-Day Package containing the SOMAVERT vials, may be stored at room temperature up to 77°F (25°C) for a single period of up to 30 days.
    - In the space provided on the carton, record the date when the carton was removed from the refrigerator and the discard date (30 days after removal from the refrigerator).
    - After the carton has been stored at room temperature, it should not be placed back into the refrigerator. If not used within 30 days at room temperature, the vials should be thrown away.
- Throw away the SOMAVERT vials after the expiration date printed on the carton or the discard date, whichever is sooner.
- The prefilled syringes may be stored at a temperature up to 86°F (30°C) until the expiration date printed on the carton. After that time, they should be thrown away.
- Do not freeze SOMAVERT.
- Read the Instructions for Use for the right way to mix SOMAVERT.
- After you mix the SOMAVERT powder and liquid:
  - Keep the mixed SOMAVERT at room temperature between 59°F to 77°F (15°C to 25°C).
  - Keep SOMAVERT inside the vial or the syringe until you are ready to inject it.
  - You must use the mixed SOMAVERT immediately after you mix it.
  - If you have not used the mixed SOMAVERT immediately, throw it away.

Keep SOMAVERT and all medicines out of the reach of children.

General information about the safe and effective use of SOMAVERT.
Medicines are sometimes prescribed for purposes other than those listed in a Patient Information leaflet. Do not use SOMAVERT for a condition for which it was not prescribed. Do not give SOMAVERT to other people, even if they have the same symptoms that you have. It may harm them.
This Patient Information summarizes the most important information about SOMAVERT. If you would like more information, talk with your healthcare provider. You can ask your pharmacist or healthcare provider for information about SOMAVERT that is written for health professionals.

What are the ingredients in SOMAVERT?
Active ingredient: pegvisomant, including polyethylene glycol
Inactive ingredients: glycine, mannitol, sodium dihydrogen phosphate monohydrate, and sodium phosphate dibasic anhydrous.

U.S. License No. 1216

LAB-0783-4.0

For more information, go to www.SOMAVERT.com or call 1-800-645-1280.

This Patient Information has been approved by the U.S. Food and Drug Administration. Revised: 7/2023

INSTRUCTIONS FOR USE

SOMAVERT® (SOM-ah-vert)
(pegvisomant)
for injection, for subcutaneous use

Read these Instructions for Use before you start using SOMAVERT and each time you get a refill. There may be new information. This leaflet does not take the place of talking to your healthcare provider about your medical condition or your treatment. Your healthcare provider should show you or a caregiver how to inject SOMAVERT the right way before you inject it for the first time.

SOMAVERT is available in two types of packaging:

- One Day Package (containing one single-dose vial of SOMAVERT powder, a prefilled syringe, and a safety needle)
- 30-Day Package (containing three intermediate cartons of 10 single-dose vials of SOMAVERT powder, 30 prefilled syringes, and 30 safety needles)
- Before you mix the SOMAVERT powder and the liquid:
  - Store SOMAVERT in a refrigerator at 36 ºF to 46 ºF (2 ºC to 8 ºC).
  - The One Day Package and intermediate cartons in the 30-Day Package containing the SOMAVERT vials, may be stored at room temperature up to 77°F (25°C) for a single period of up to 30 days.
    - In the space provided on the carton, record the date when the carton was removed from the refrigerator and the discard date (30 days after removal from the refrigerator).
    - After the carton has been stored at room temperature, it should not be placed back into the refrigerator. If not used within 30 days at room temperature, the vials should be thrown away.
- Throw away the SOMAVERT vials after the expiration date printed on the carton or the discard date, whichever is sooner.
- The prefilled syringes may be stored at a temperature up to 86°F (30°C) until the expiration date printed on the carton. After that time, they should be thrown away.
- Do not freeze SOMAVERT.

Important:

- Do not share your SOMAVERT syringes or needles with other people. You may give other people a serious infection, or get an infection from them.
- SOMAVERT comes in a vial as a white block of powder. You must mix SOMAVERT with a liquid (diluent) before you can use it. The liquid comes in a single-dose prefilled syringe labeled 'Sterile Water for Injection'. Do not use any other liquid to mix with SOMAVERT.
- You must use the mixed SOMAVERT immediately after you mix it. If you have not used the mixed SOMAVERT immediately, throw it away.

Step 1. Things you need

- A vial of SOMAVERT powder.
- A prefilled syringe.
- A safety needle.

You will also need:

- A cotton ball.
- An alcohol swab.
- A sharps disposal container. See "Dispose" at the end of these instructions.

Step 2. Getting ready

Before you start:

- Only mix SOMAVERT and the liquid when you are ready to inject your dose.
- SOMAVERT One Day Package: If refrigerated, remove the package and allow it to come to room temperature in a safe place for at least 10 minutes before you need to use it.
- SOMAVERT 30-Day Package: If refrigerated, remove a single vial from the intermediate carton and allow it to come to room temperature in a safe place for at least 10 minutes before you need to use it.
- Do not heat the vial or syringe by using a heat source such as hot water or microwave. Let it warm up on its own.
- Wash your hands with soap and water, and dry completely.
- Peel open the packaging of the syringe and safety needle to make it easier to pick up each item as you prepare for your injection.
- Do not use the syringe or vial if:
  - they are damaged or faulty
  - the expiration date has passed
  - it has been frozen, even if it has now thawed (syringe only)

Step 3. Choose injection area

- Choose a different location within an area for each injection.
- Avoid bony areas or areas that are bruised, red, sore or hard, or areas that have scars or skin conditions.
- Clean the injection area with the alcohol swab as instructed by your healthcare provider.
- Allow the injection area to dry.

Step 4. Remove vial cap

- Remove the cap from the vial.
- Throw the cap away. It is not needed again.
  Caution: Do not let anything touch the vial stopper.

Step 5. Remove syringe cap

- Snap off the syringe cap leaving the syringe collar in place. It may take more effort to snap off than you might expect.
- Throw the syringe cap away. It is not needed again.
- Keep the syringe upright to avoid leakage.
  Caution: Do not let the end of the syringe touch anything when the syringe cap is off.

Step 6. Attach safety needle

- Push down and twist the safety needle firmly onto the syringe as far as it will go.

Step 7. Remove needle cover

- Fold the needle guard out of the way of the needle cover.
- Carefully pull the needle cover straight off.
- Throw the needle cover away. It is not needed again.
  Caution: Do not let the needle touch anything.

Step 8. Insert needle

- Push the needle through the center of vial stopper, as shown.
- Support the syringe while the needle is in the vial stopper to prevent bending the needle.

Step 9. Add liquid

- Tilt both the vial and syringe at an angle, as shown.
- Push the plunger rod down slowly until all the liquid has emptied into the vial.
- Caution: Do not squirt the liquid directly onto the powder. This creates foam. Foam makes the medicine unusable.
- Do not withdraw the needle yet.

Step 10. Swirl vial

- Support both the syringe and vial in 1 hand, as shown.
- Gently and slowly swirl the liquid, sliding the vial in a circular motion on a flat surface.
- Continue swirling the liquid until all the powder has fully dissolved.
  Note: This may take up to 5 minutes.
  Do not shake.

Step 11. Check medicine

- Keeping the needle in the vial, look carefully at the medicine. It must be clear and free of particles.
- Do not use if:
  - the medicine is cloudy or hazy
  - the medicine has any color at all
  - there are any particles or foam in the vial
- If you have any doubts about your medication go to www.SOMAVERT.com or call 1-800-645-1280.

Step 12. Reposition needle

- Turn the vial so that you can see the stopper gap, as shown.
- Pull the needle down so that the needle tip is at the lowest point in the liquid. This will help you to draw off as much liquid as possible.
- Check that the plunger rod has not moved. If the plunger rod has moved, then push it back all the way into the syringe. This ensures that all air is removed from the syringe before you draw off the dose.

Step 13. Draw off dose

- Slowly pull back the plunger rod to withdraw as much medicine as possible from the vial.
  Note: If you see air in the syringe, tap the barrel to float the bubbles to the top, and then gently push the bubbles out into the vial.
- Pull the needle out of the vial.

Step 14. Insert needle

- Gently pinch the skin at the site of injection.
- Insert the needle to its full depth into the pinched skin.

Step 15. Inject medicine

- Push the plunger rod down slowly until the barrel is empty.
  Note: Make sure you keep the needle in at full depth.
- Release the pinched skin and pull the needle straight out.

Step 16. Make needle safe

- Fold the needle guard over the needle.
  Gently apply pressure using a hard surface to lock the needle guard in place.
- Note: You will hear a click when the needle guard has been locked.

Step 17. Dispose

- Put your used syringes in a FDA cleared sharps disposal container right away after use.
- Do not throw away (dispose of) syringes in your household trash.
  Note: If you do not have a FDA cleared sharps disposal container, please refer to the safe syringe disposal information on the right hand side of this leaflet.

Step 18. After injection

- If necessary, use a clean cotton ball and press lightly on the injection area.
- Do not rub the area.

QUESTIONS AND ANSWERS

What should I do if anything has accidentally touched the vial stopper?

- Clean the vial stopper with a fresh alcohol wipe, and leave it to dry completely. If you are unable to clean the stopper, do not use the vial.

What should I do with the syringe if it has been dropped?

- Do not use it even if it looks undamaged. Dispose of the syringe in the same way as a used syringe. You will need a replacement syringe.

How many times can I safely insert the needle into the vial stopper?

- Only 1 time. Withdrawing and reinserting greatly increases the risk of needle damage, and will blunt the needle. This can cause discomfort and increases risk of skin damage and infection. There is also a risk you may lose some of the medicine.

Is it okay to shake the vial if the powder is not dissolving?

- No. Never shake the vial. Shaking can destroy the medicine and create foam. The powder may take a few minutes to dissolve fully, so continue swirling the vial gently until the liquid is completely clear.

How can I tell if there is any foam in the vial?

- Foam looks like a mass of small bubbles that float as a layer to the top of the liquid. Do not inject SOMAVERT if it has foamed.

How can I prevent the medicine from foaming?

- Press the plunger very slowly so that the liquid gently runs down the inside of the vial. Do not spray the liquid directly onto the powder, because this creates foam. This will also reduce the swirling time and allow more of the medicine to be drawn off.

I can see some air in the syringe. Is this okay?

- Tiny air bubbles in the liquid are normal and are safe to inject. However, it is possible to accidently draw air into the syringe, which should be removed before injecting. Bubbles or air gaps that float to the top of the liquid should be pushed back out into the vial.

Why can I not get all of the medicine out of the vial?

- The shape of the vial means that a very small amount of the medicine will be left behind in the vial. This is normal. To ensure that only a trace of medicine remains, make sure the needle tip is as low as it can be in the vial when drawing off your dose.

What should I do if I have any doubts about my medicine?

- For more information, go to www.SOMAVERT.com or call 1-800-645-1280.

Safe syringe disposal information

If you do not have a FDA-cleared sharps disposal container, you may use a household container that is:

- made of heavy-duty plastic,
- can be closed with a tight-fitting, puncture-resistant lid, without sharps being able to come out,
- upright and stable during use, leak-resistant, and
- properly labeled to warn of hazardous waste inside the container.

When your sharps disposal container is almost full, you will need to follow your community guidelines for the right way to dispose of your sharps disposal container. There may be state or local laws about how you should throw away used needles and syringes.

For more information about safe sharps disposal, and for specific information about sharps disposal in the state that you live in, go to the FDA's website at: http://www.fda.gov/safesharpdisposal

This Instructions for Use has been approved by the U.S. Food and Drug Administration.

U.S. License No. 1216
LAB-0784-3.0
Revised: July 2023

PRINCIPAL DISPLAY PANEL - 1 mL Syringe Label

1 mL SINGLE-DOSE
NDC 0009-5936-01

Sterile Water for Injection, USP

For reconstitution of SOMAVERT®
Contains no antimicrobial or other
added substance. Sterile, nonpyrogenic.

Manufactured by
Pharmacia & Upjohn Company LLC
A subsidiary of Pfizer Inc.
New York, NY 10001
U.S. License No. 1216

LOT/EXP
Rx only

PAA213086

PRINCIPAL DISPLAY PANEL - 10 mg Vial Label

NDC 0009-5175-02

Pfizer

Somavert®
(pegvisomant) for injection

10 mg/vial

For Subcutaneous Use Only

One Single-Dose Vial
Discard unused portion.

Rx only

PAA213088

PRINCIPAL DISPLAY PANEL - Kit Carton - 7166-01

NDC 0009-7166-01

Pfizer

Somavert®
(pegvisomant) for injection

10 mg/vial

For Subcutaneous Injection Only

One Single-Dose Vial
Discard unused portion.
Contents: One Somavert single-dose vial, one diluent prefilled
syringe containing 1 mL Sterile Water for Injection, USP and
one 27 gauge ½ inch safety needle.

Rx only

PRINCIPAL DISPLAY PANEL - 10 mg Vial Carton

NDC 0009-5175-10

Pfizer

Somavert®
(pegvisomant) for injection

10 mg/vial

For Subcutaneous Injection Only

Single-Dose Vials
Discard unused portion.

Contents of intermediate carton:
Ten single-dose vials of Somavert

Rx only

PRINCIPAL DISPLAY PANEL - Kit Carton - 7166-30

NDC 0009-7166-30

Pfizer
Somavert®
(pegvisomant) for injection

10 mg/vial

For Subcutaneous Injection Only

Single-Dose Vials
Discard unused portion.
Contents of outer carton:
Three intermediate cartons (each containing ten single-dose vials of
Somavert), thirty diluent prefilled syringes containing 1 mL Sterile
Water for Injection, USP and thirty 27 gauge ½ inch safety needles.

Rx only

PRINCIPAL DISPLAY PANEL - 15 mg Vial Label

NDC 0009-5177-02

Pfizer

Somavert®
(pegvisomant) for injection

15 mg/vial

For Subcutaneous Use Only

One Single-Dose Vial
Discard unused portion.

Rx only

PAA213202

PRINCIPAL DISPLAY PANEL - Kit Carton - 7168-01

NDC 0009-7168-01

Pfizer

Somavert®
(pegvisomant) for injection

15 mg/vial

For Subcutaneous Injection Only

One Single-Dose Vial
Discard unused portion.
Contents: One Somavert single-dose vial, one diluent prefilled
syringe containing 1 mL Sterile Water for Injection, USP and
one 27 gauge ½ inch safety needle.

Rx only

PRINCIPAL DISPLAY PANEL - 15 mg Vial Carton

NDC 0009-5177-10

Pfizer

Somavert®
(pegvisomant) for injection

15 mg/vial

For Subcutaneous Injection Only

Single-Dose Vials
Discard unused portion.

Contents of intermediate carton:
Ten single-dose vials of Somavert

Rx only

PRINCIPAL DISPLAY PANEL - Kit Carton - 7168-30

NDC 0009-7168-30

Pfizer

Somavert®
(pegvisomant) for injection

15 mg/vial

For Subcutaneous Injection Only

Single-Dose Vials
Discard unused portion.
Contents of outer carton:
Three intermediate cartons (each containing ten single-dose
vials of Somavert), thirty diluent prefilled syringes containing
1 mL Sterile Water for Injection, USP and thirty 27 gauge ½
inch safety needles.

Rx only

PRINCIPAL DISPLAY PANEL - 20 mg Vial Label

NDC 0009-5179-02

Pfizer

Somavert®
(pegvisomant) for injection

20 mg/vial

For Subcutaneous Use Only

One Single-Dose Vial
Discard unused portion.

Rx only

PAA213206

PRINCIPAL DISPLAY PANEL - Kit Carton - 7188-01

NDC 0009-7188-01

Pfizer

Somavert®
(pegvisomant) for injection

20 mg/vial

For Subcutaneous Injection Only

One Single-Dose Vial
Discard unused portion.

Contents: One Somavert single-dose vial, one diluent prefilled
syringe containing 1 mL Sterile Water for Injection, USP and
one 27 gauge ½ inch safety needle.

Rx only

PRINCIPAL DISPLAY PANEL - 20 mg Vial Carton

NDC 0009-5179-10

Pfizer

Somavert®
(pegvisomant) for injection

20 mg/vial

For Subcutaneous Injection Only

Single-Dose Vials
Discard unused portion.

Contents of intermediate carton:
Ten single-dose vials of Somavert

Rx only

PRINCIPAL DISPLAY PANEL - Kit Carton - 7188-30

NDC 0009-7188-30

Pfizer

Somavert®
(pegvisomant) for injection

20 mg/vial

For Subcutaneous Injection Only

Single-Dose Vials
Discard unused portion.

Contents of outer carton:
Three intermediate cartons (each containing ten single-dose
vials of Somavert), thirty diluent prefilled syringes containing 1 mL
Sterile Water for Injection, USP and thirty 27 gauge ½ inch
safety needles.

Rx only

PRINCIPAL DISPLAY PANEL - 25 mg Vial Label

NDC 0009-5201-04

Pfizer

Somavert®
(pegvisomant) for injection

25 mg/vial

For Subcutaneous Use Only

One Single-Dose Vial
Discard unused portion.

Rx only

PAA213210

PRINCIPAL DISPLAY PANEL - Kit Carton - 7199-01

NDC 0009-7199-01

Pfizer

Somavert®
(pegvisomant) for injection

25 mg/vial

For Subcutaneous Injection Only

One Single-Dose Vial
Discard unused portion.
Contents: One Somavert single-dose vial, one diluent prefilled
syringe containing 1 mL Sterile Water for Injection, USP and
one 27 gauge ½ inch safety needle.

Rx only

PRINCIPAL DISPLAY PANEL - 25 mg Vial Carton

NDC 0009-5201-10

Pfizer

Somavert®
(pegvisomant) for injection

25 mg/vial

For Subcutaneous Injection Only

Single-Dose Vials
Discard unused portion.

Contents of intermediate carton:
Ten single-dose vials of Somavert

Rx only

PRINCIPAL DISPLAY PANEL - Kit Carton - 7199-30

NDC 0009-7199-30

Pfizer

Somavert®
(pegvisomant) for injection

25 mg/vial

For Subcutaneous Injection Only

Single-Dose Vials
Discard unused portion.

Contents of outer carton:
Three intermediate cartons (each containing ten single-dose
vials of Somavert), thirty diluent prefilled syringes containing
1 mL Sterile Water for Injection, USP and thirty 27 gauge ½ inch
safety needles.

Rx only

PRINCIPAL DISPLAY PANEL - 30 mg Vial Label

NDC 0009-5376-04

Pfizer

Somavert®
(pegvisomant) for injection

30 mg/vial

For Subcutaneous Use Only

One Single-Dose Vial
Discard unused portion.

Rx only

PAA213244

PRINCIPAL DISPLAY PANEL - Kit Carton - 7200-01

NDC 0009-7200-01

Pfizer

Somavert®
(pegvisomant) for injection

30 mg/vial

For Subcutaneous Injection Only

One Single-Dose Vial
Discard unused portion.
Contents: One Somavert single-dose vial, one diluent prefilled
syringe containing 1 mL Sterile Water for Injection, USP and
one 27 gauge ½ inch safety needle.

Rx only

PRINCIPAL DISPLAY PANEL - 30 mg Vial Carton

NDC 0009-5376-10

Pfizer

Somavert®
(pegvisomant) for injection

30 mg/vial

For Subcutaneous Injection Only

Single-Dose Vials
Discard unused portion.

Contents of intermediate carton:
Ten single-dose vials of Somavert

Rx only

PRINCIPAL DISPLAY PANEL - Kit Carton - 7200-30

NDC 0009-7200-30

Pfizer

Somavert®
(pegvisomant) for injection

30 mg/vial

For Subcutaneous Injection Only

Single-Dose Vials
Discard unused portion.
Contents of outer carton:
Three intermediate cartons (each containing ten single-dose
vials of Somavert), thirty diluent prefilled syringes containing 1 mL
Sterile Water for Injection, USP and thirty 27 gauge ½ inch safety
needles.

Rx only